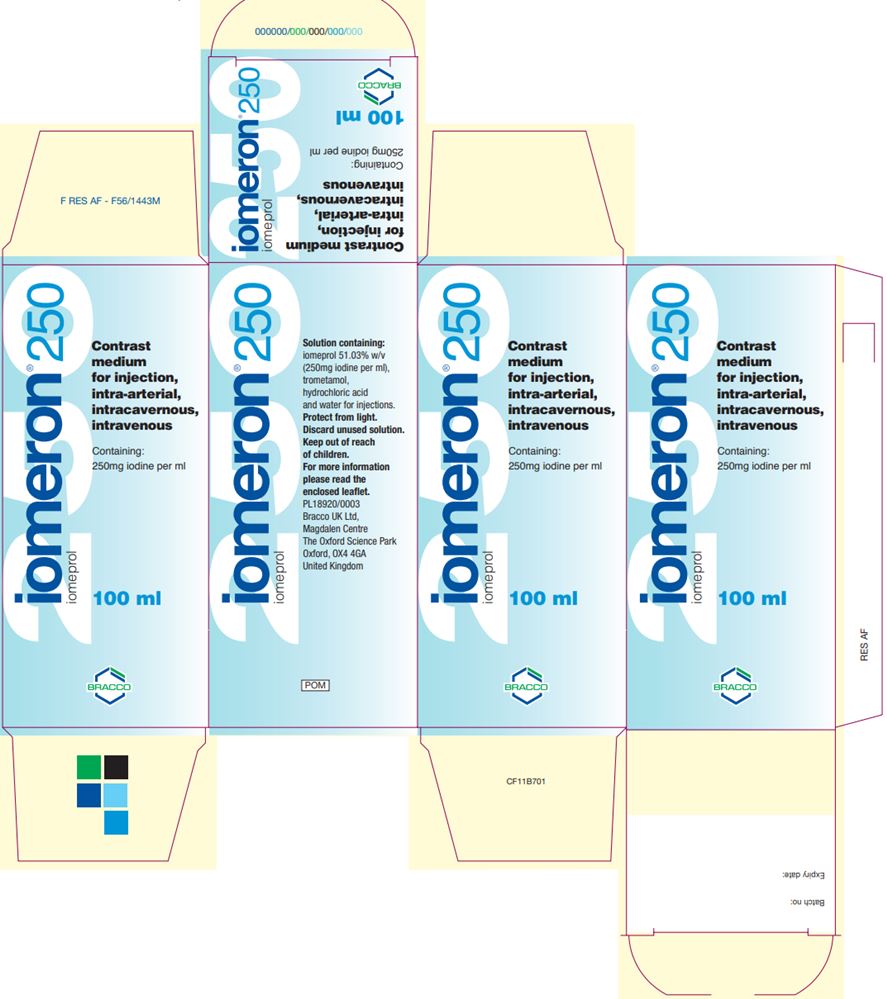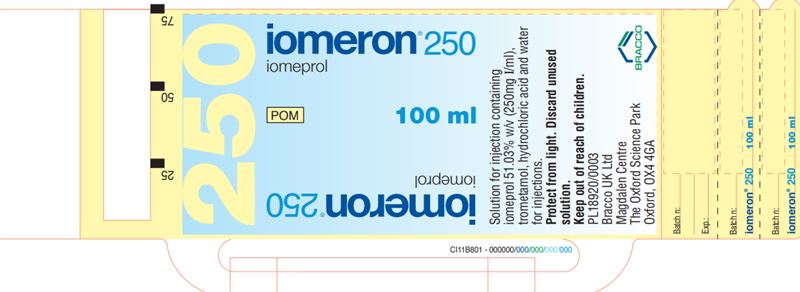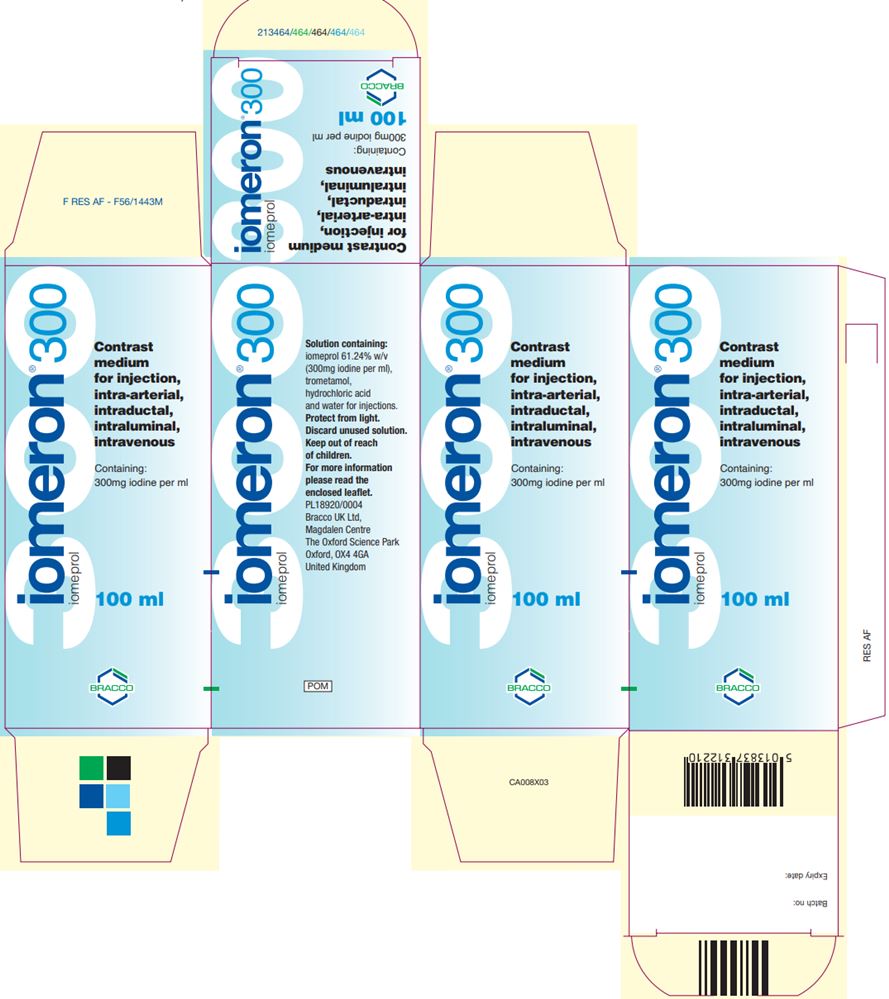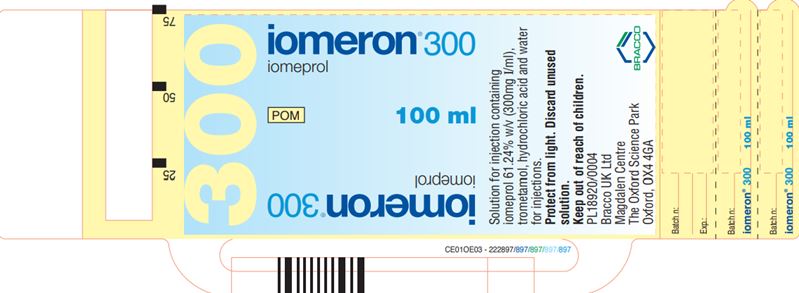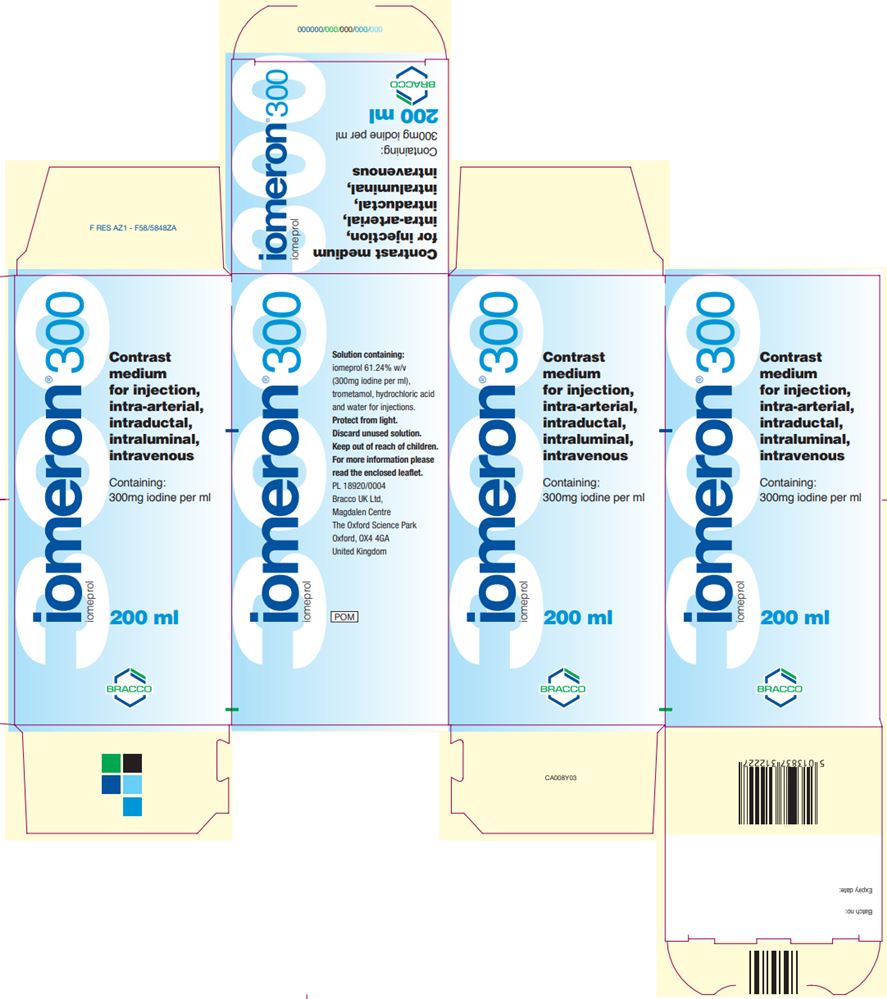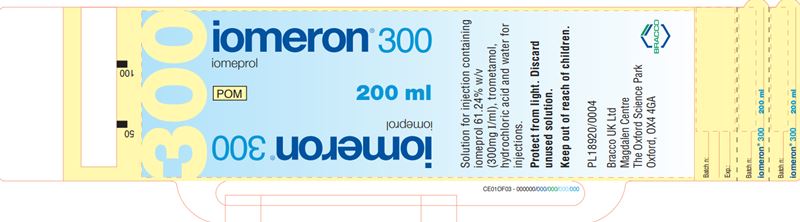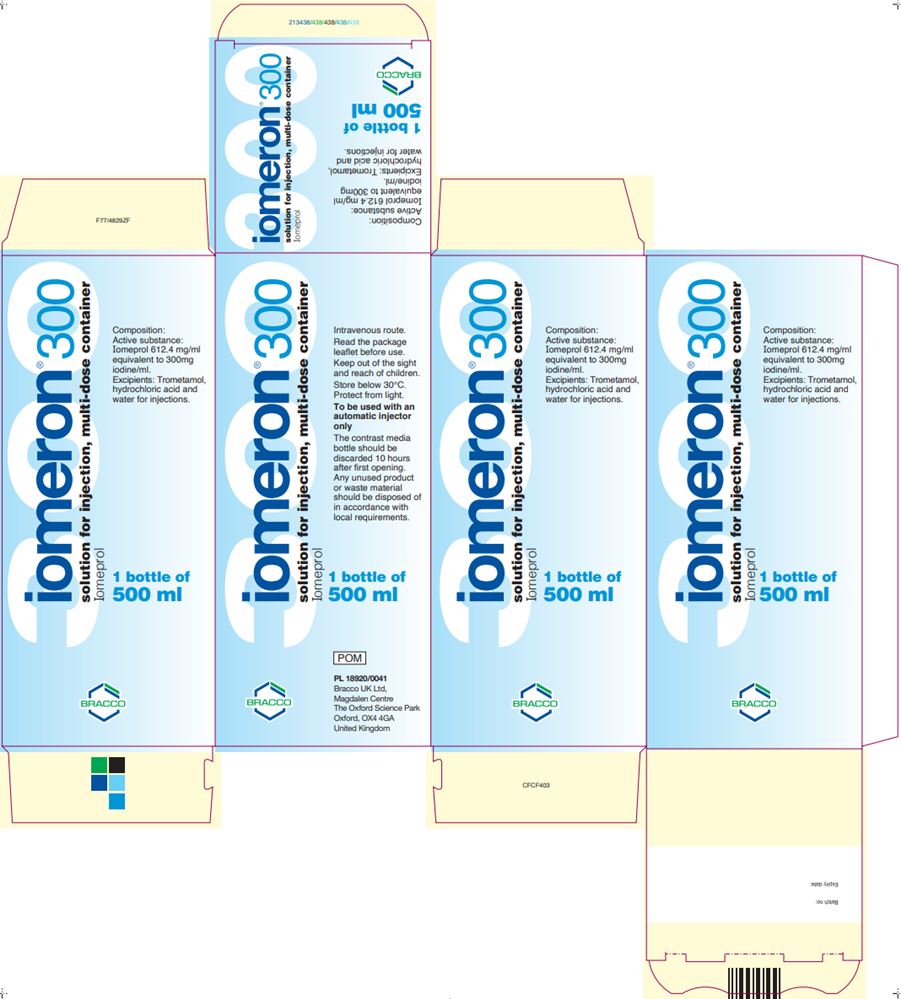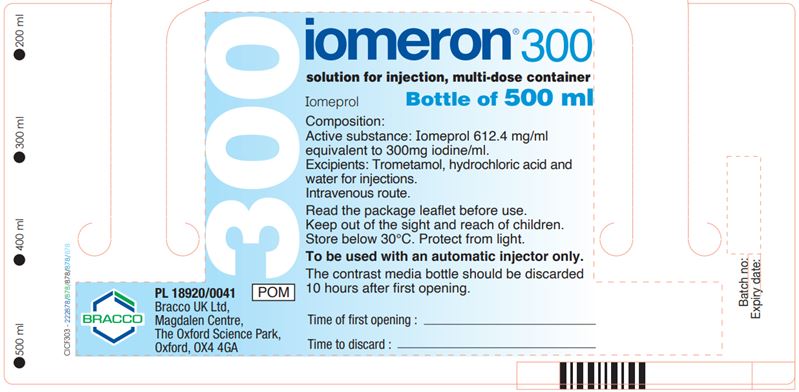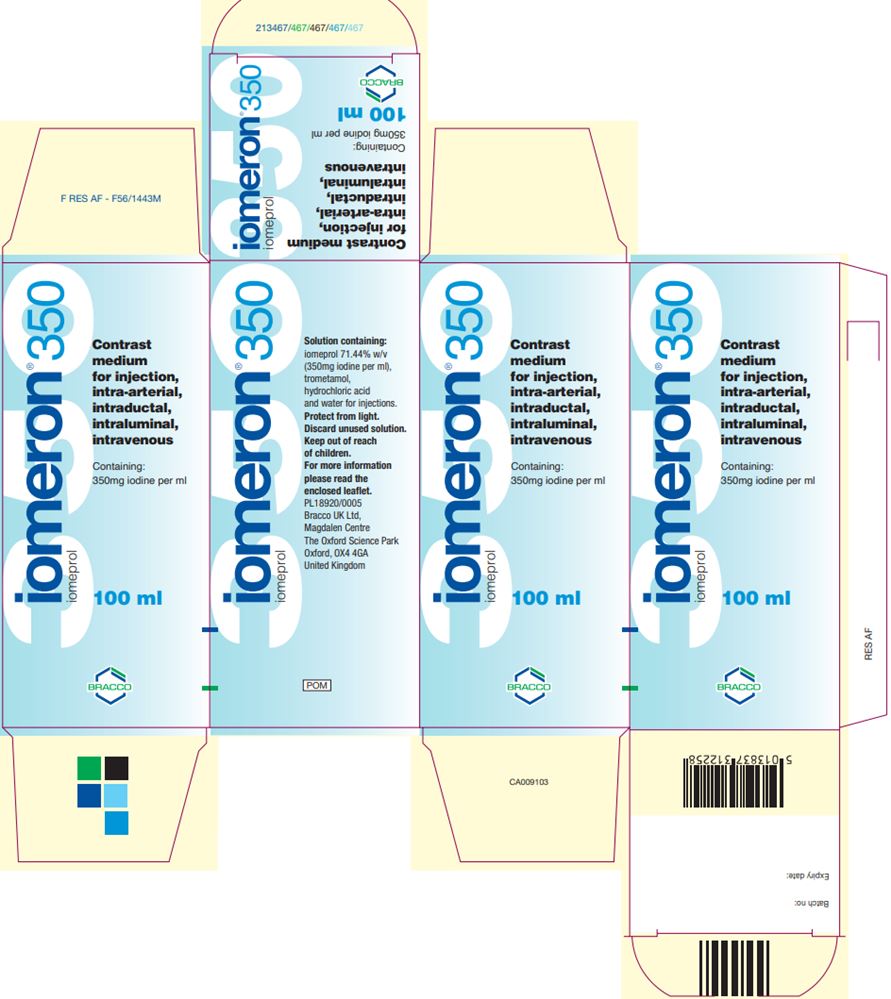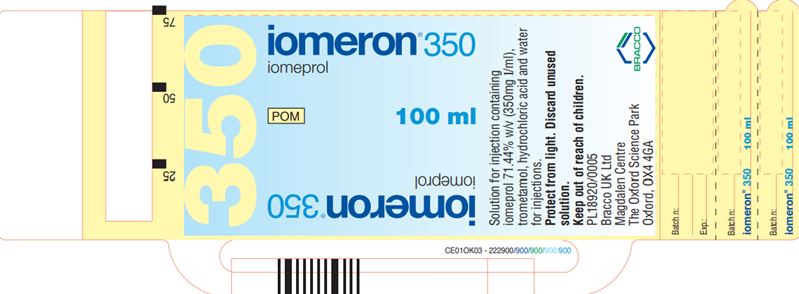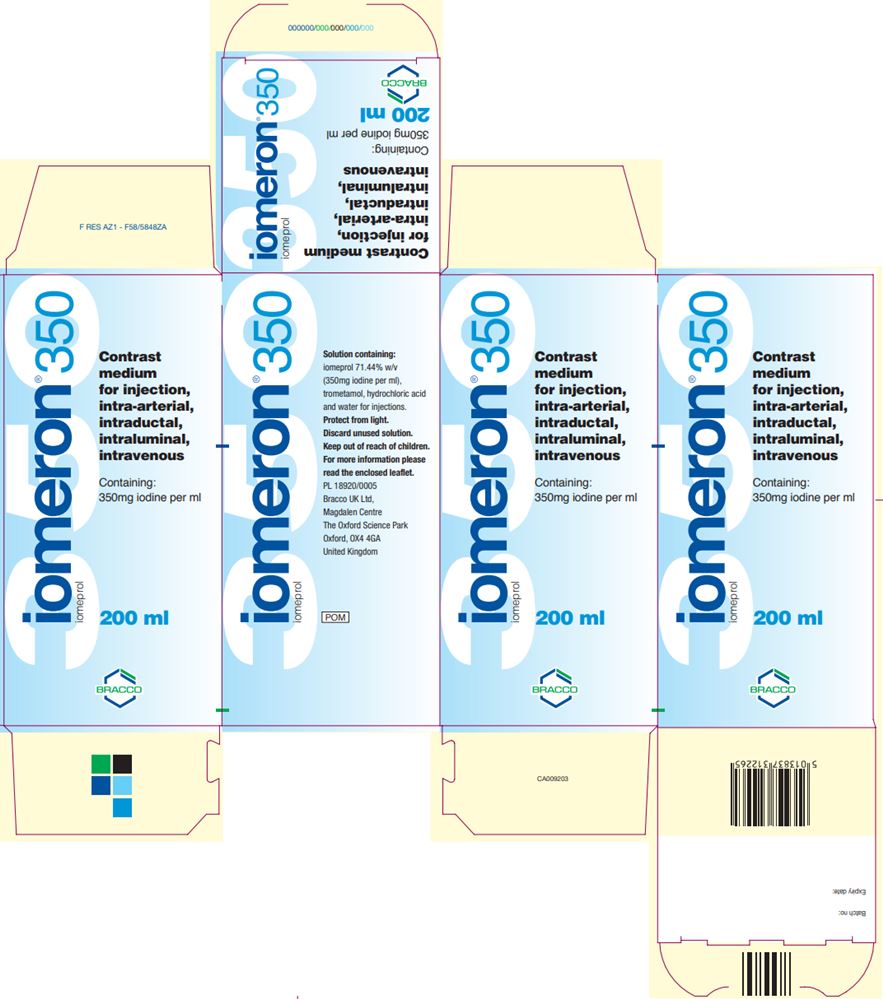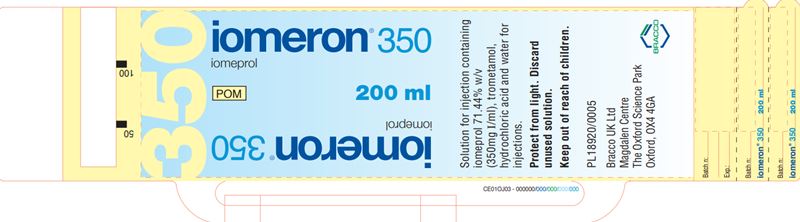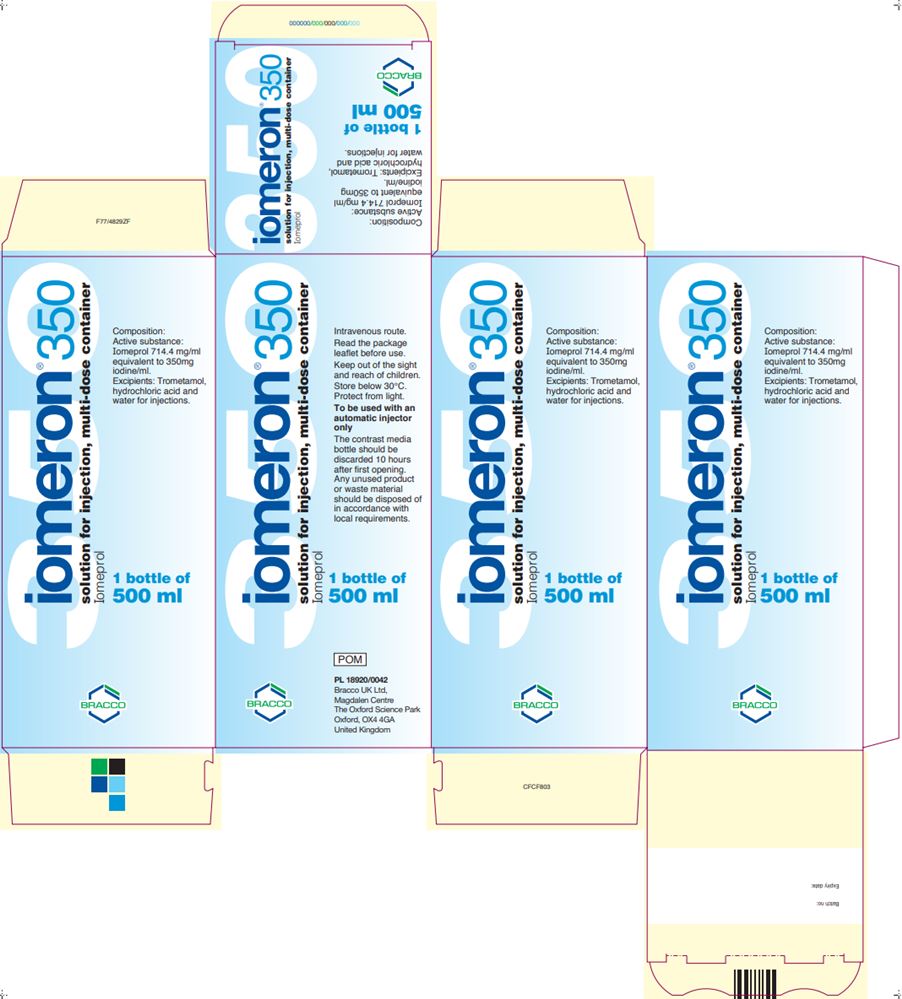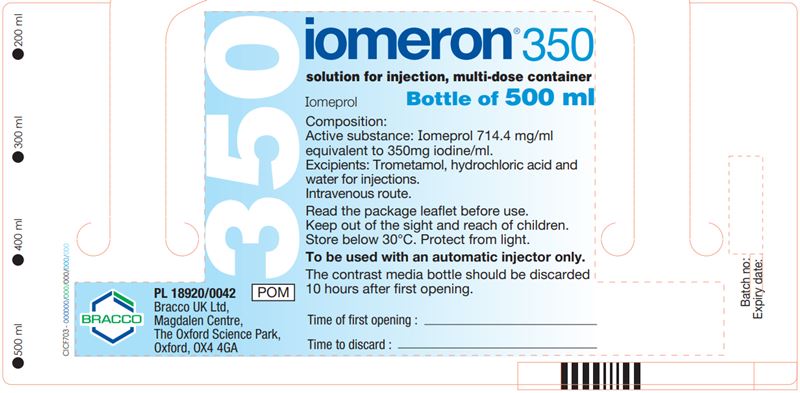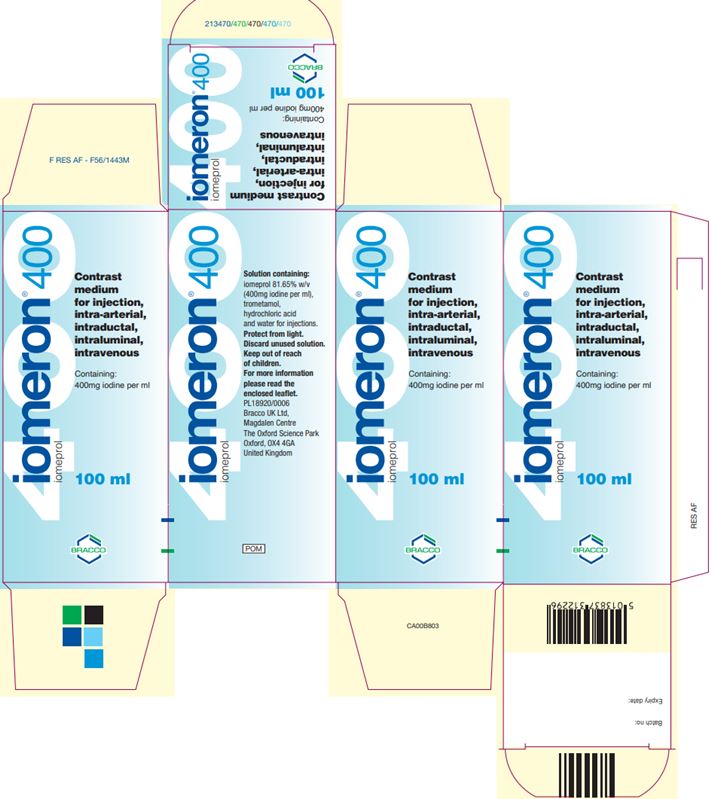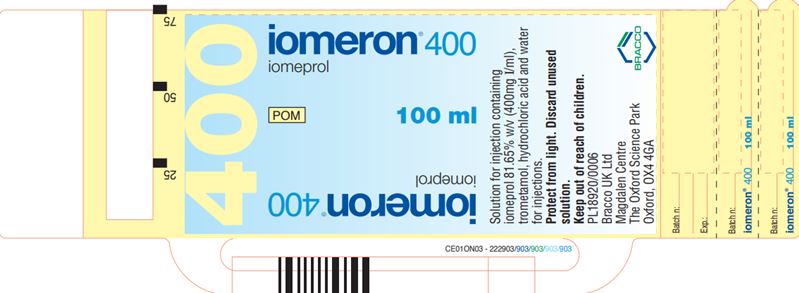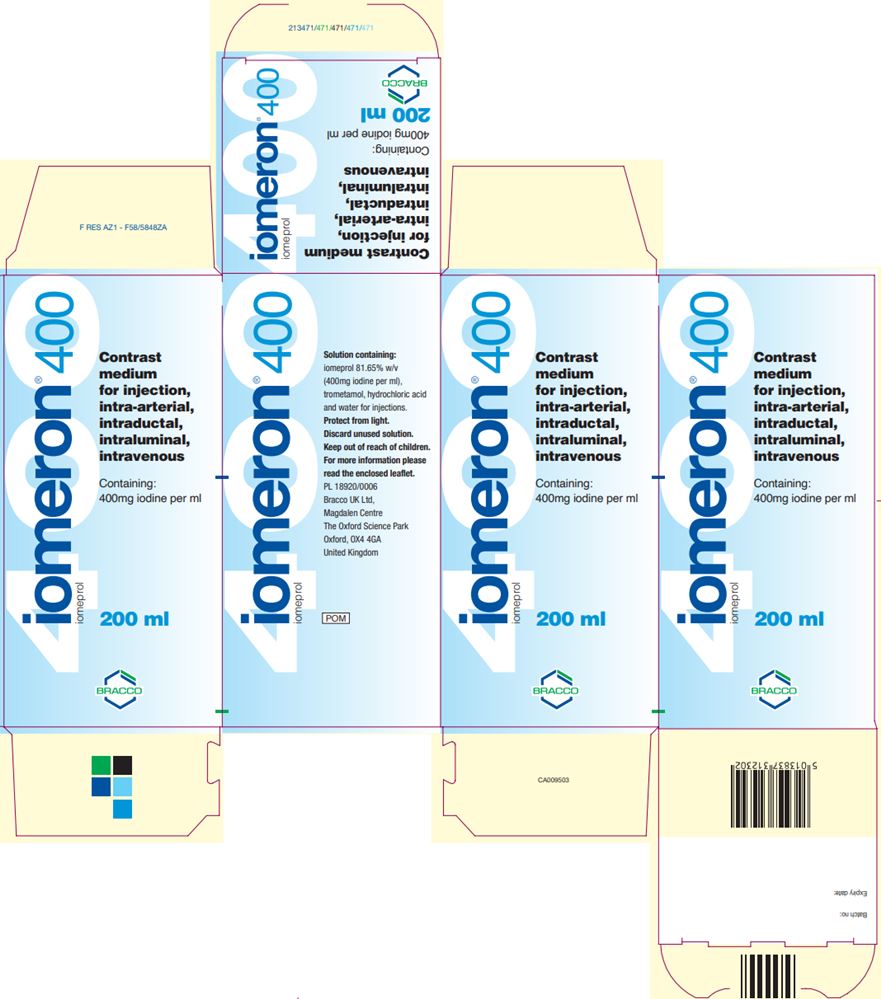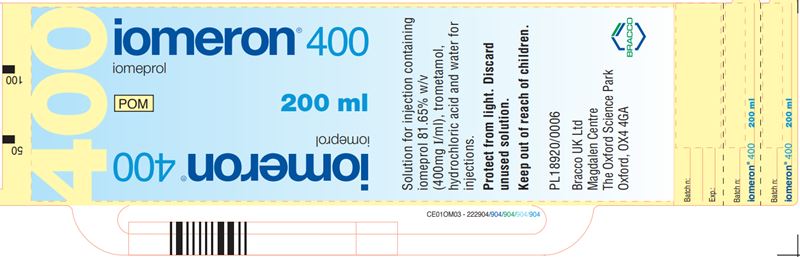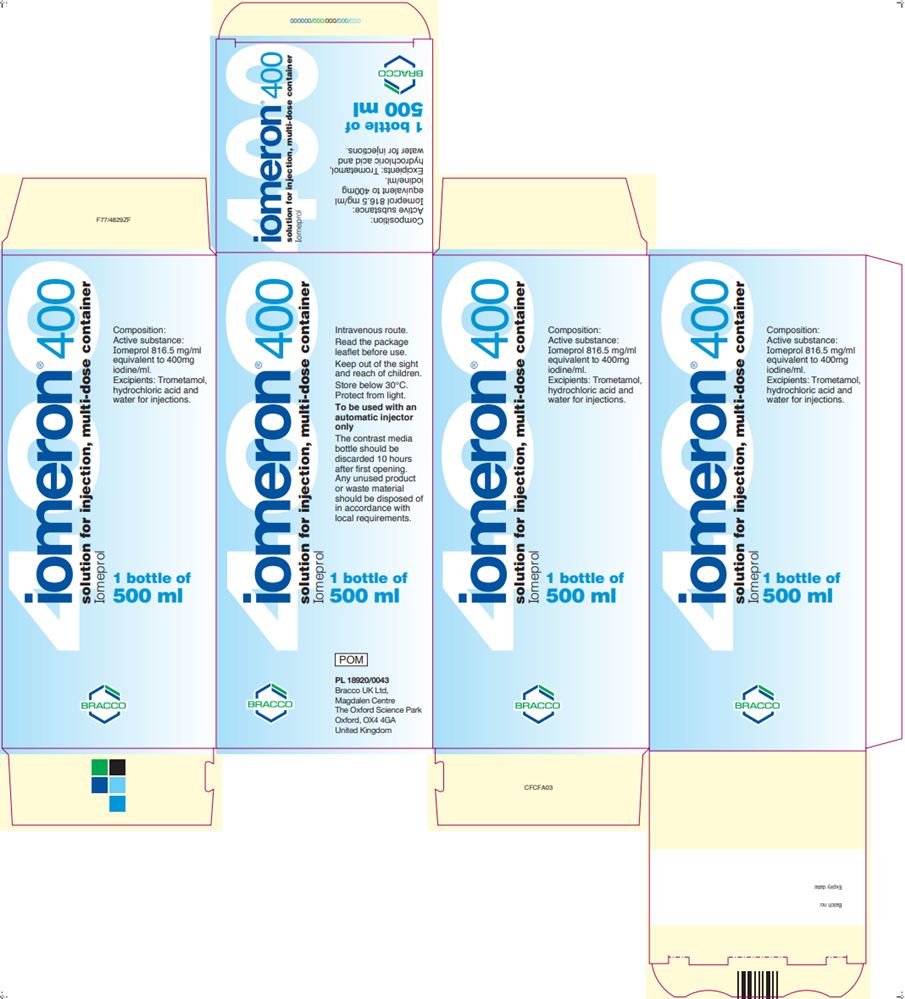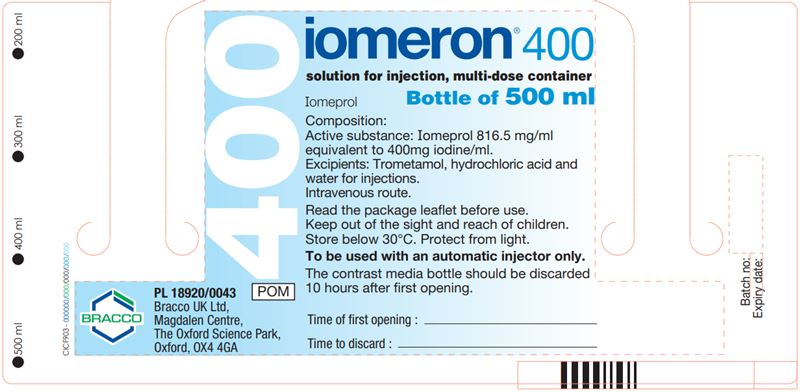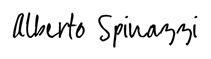 DRUG LABEL: Iomeron
NDC: 76381-725 | Form: INJECTION, SOLUTION
Manufacturer: BIPSO GmbH
Category: prescription | Type: HUMAN PRESCRIPTION DRUG LABEL
Date: 20251119

ACTIVE INGREDIENTS: IOMEPROL 510 mg/1 mL
INACTIVE INGREDIENTS: TROMETHAMINE; HYDROCHLORIC ACID; WATER

HEALTH CARE PROVIDER LETTER

IMPORTANT DRUG INFORMATION
may be found at the following link:
https://imaging.bracco.com/us-en/products/ct-ct-colonography/iomeron

July 6, 2022

Subject: Temporary importation of Iomeron® (iomeprol injection) to address drug shortage issues

Dear Healthcare Professional,

Due to the current critical shortages of Omnipaque™ (iohexol injection), Visipaque™ (iodixanol injection), and Ultravist (iopromide injection) in the U.S. market, Bracco Diagnostics Inc. (hereafter “Bracco”) is coordinating with the U.S. Food and Drug Administration (FDA) to increase the availability of iodinated contrast media indicated for intravascular use.

Accordingly, Bracco has initiated temporary importation of Iomeron® (iomeprol injection), an intravascular iodinated contrast medium, into the U.S. market. This product will be used in adult patients by intravenous or intraarterial route of administration only during the shortage. FDA has not approved Iomeron (iomeprol). Iomeron (iomeprol) drug product is manufactured by BIPSO GmbH in Germany and Patheon Italia S.p.A. in Italy. These facilities are also used to manufacture Bracco’s FDA-approved intravascular iodinated contrast medium Isovue (iopamidol injection).

FDA’s regulatory discretion for the importation and distribution of Iomeron (iomeprol) is limited to Bracco during the critical U.S. shortages of Omnipaque, Visipaque, and Ultravist.

Effective immediately, and during this temporary period, Bracco will offer the following presentations of Iomeron (iomeprol) to the U.S. market:

Product Description | Iodine Concentration (mg iodine/mL) | Package Size | Lot Number | Label Language | NDC Number | UK SmPC
Iomeron (iomeprol injection) 250 | 250 | 56 X 100 mL | 2C42685 | French | 0270-7250-10 | Iomeron 300 UK SmPC SD
Iomeron (iomeprol injection) 300 | 300 | 56 X 100 mL | 2C43416 KP1552A | French | 0270-7300-10 | Iomeron 300 UK SmPC SD
Iomeron (iomeprol injection) 300 | 300 | 10 X 200 mL | KP2701F | English | 0270-7300-20 | Iomeron 300 UK SmPC SD
Iomeron (iomeprol injection) 300 | 300 | 6 X 500 mL | KP2804A | Spanish | 0270-9300-06 | Iomeron 300 UK SmPC MD
Iomeron (iomeprol injection) 350 | 350 | 56 X 100 mL | LP1566C | Russian | 0270-7350-10 | Iomeron 350 UK SmPC SD
Iomeron (iomeprol injection) 350 | 350 | 30 X 150 mL | 2C42507 | French | 0270-7350-15 | Iomeron 350 UK SmPC SD
Iomeron (iomeprol injection) 350 | 350 | 10 X 200 mL | LP2705A | English | 0270-7350-20 | Iomeron 350 UK SmPC SD
Iomeron (iomeprol injection) 350 | 350 | 6 X 500 mL | LP2807A | Spanish | 0270-9350-06 | Iomeron 350 UK SmPC MD
Iomeron (iomeprol injection) 350 | 350 | 9 X 500 mL | LP2810B | English | 0270-9350-09 | Iomeron 350 UK SmPC MD
Iomeron (iomeprol injection) 400 | 400 | 56 X 100 mL | MP1577A | Russian | 0270-7400-13 | Iomeron 400 UK SmPC SD
Iomeron (iomeprol injection) 400 | 400 | 10 X 100 mL | MP2561C | Portuguese | 0270-7400-10 | Iomeron 400 UK SmPC SD
Iomeron (iomeprol injection) 400 | 400 | 56 X 100 mL | MP2556A | Polish | 0270-7400-16 | Iomeron 400 UK SmPC SD
Iomeron (iomeprol injection) 400 | 400 | 30 X 200 mL | MP2702C | Slovenian | 0270-7400-20 | Iomeron 400 UK SmPC SD
Iomeron (iomeprol injection) 400 | 400 | 9 X 500 mL | MP2807C | English | 0270-9400-01 | Iomeron 400 UK SmPC MD
Iomeron (iomeprol injection) 400 | 400 | 6 X 500 mL | MP2806A | English | 0270-9400-06 | Iomeron 400 UK SmPC MD
Iomeron (iomeprol injection) 400 | 400 | 9 X 500 mL | MP2807A | Portuguese | 0270-9400-03 | Iomeron 400 UK SmPC MD

The imported Iomeron (iomeprol) was originally labelled for use in countries outside the United States. The bottle and box labels will display the text used when marketing Iomeron (iomeprol) in those countries. Note that:

- The prescribing information will be provided with each bottle of Iomeron (iomeprol), in the form of the appropriate Summary of Product Characteristics (SmPC) document approved for the U.K., which is written in English, and is representative of all Iomeron (iomeprol) SmPCs for that presentation.
- Copies of the U.K. SmPCs accompany this letter, along with images of the U.K. bottle and box labels that will be imported.
- The Iomeron (iomeprol) U.K. SmPCs are available on-line at: https://imaging.bracco.com/us-en/products/ct-ct-colonography/iomeron
- For those bottles and box labels not in English, English translations of these labels are available on-line at: https://imaging.bracco.com/us-en/products/ct-ct-colonography/iomeron

There are differences among the currently marketed nonionic, low-osmolar iodinated contrast media in their physico-chemical properties, as can be seen in the below table that compares them at the concentration of 300 mg iodine/mL (except for Visipaque, for which the nearest concentration is 320 mg iodine/mL):

Table of Physico-chemical Properties of Iomeron (iomeprol) vs. Comparable U.S. Marketed Products (using a concentration of 300 mg iodine/mL or nearest equivalent)
Product | Viscosity (CP) |  | Osmolality (mOsm/kg water) | Density | pH
Product | 20°C | 37°C | 37°C | 37°C
Iomeron (iomeprol injection) 300 | 8.1 | 4.5 | 521 | 1.334 | 6.5 – 7.2
Iomeron (iomeprol injection) 300 | 8.8 | 4.7 | 616 | 1.339 | 6.5 – 7.5
Omnipaque (iohexol injection) 300 | 11.8 | 6.3 | 672 | 1.349 | 6.8 – 7.7
Optiray (ioversol injection) 300 | 8.2 (25°C) | 5.5 | 651 | 1.352 | 6.0 – 7.4
Visipaque (iodixanol injection) 320 | 26.6 | 11.8 | 290 | 1.356 | 6.8 – 7.7
Ultravist (iopromide injection) 300 | 9.2 | 4.9 | 607 | 1.322 | 6.5 – 8.0

Iomeron multi-dose container’s administration:

The 500 mL presentations of Iomeron are multi-dose containers. The U.K. SmPC states that the Iomeron multi-dose bottle stopper should be pierced only once, and that proper withdrawal cannulas for piercing the stopper and drawing up the contrast medium should be used. For those injectors in which the Iomeron container would be directly inserted (i.e., there would be no use of a transfer set), the injector manufacturer’s procedures for insertion should be followed, keeping in mind that the bottle stopper should be pierced only once.

Microbial contamination studies were performed where Iomeron solutions in multi-dose containers were inoculated with micro-organisms. These studies demonstrated that Iomeron solutions are bacteriostatic, with microbial growth not observed over the 10-hour period of the studies. Based upon these studies, when the 500 mL multi-dose container is used to draw up or administer separate doses of Iomeron, any unused product remaining in the bottle after 10 hours from the stopper being pierced must be discarded.

Please see Appendix 1 of this letter for tables showing the differences among the FDA-approved intra-arterial and intravenous indications for Omnipaque (iohexol), Visipaque (iodixanol), Ultravist (iopromide) and Isovue (iopamidol) vs. the intra-arterial and intravenous indications for Iomeron (iomeprol) approved in the U.K.

Iomeron (iomeprol) will be available only by prescription in the U.S. However, the imported lots do not have the statement “Rx only” on their labeling. Please refer to the Iomeron (iomeprol) U.K. SmPC for the product’s full prescribing information. In addition, please note the following comments and recommendations:

- There are differences between indications for Iomeron (iomeprol) approved in the U.K. and approved indications for iodinated contrast media (ICM) in the US. Tables comparing indications for selected FDA approved ICM and Iomeron (iomeprol) are provided in Appendix 1.
- We recommend that imported Iomeron (iomeprol) be administered only by intravenous and intra-arterial routes.
- We recommend that imported Iomeron (iomeprol) be used only in adult patients. Iomeron (iomeprol) adult dosing per the U.K. SmPC is provided in Appendix 2.
- Obtain a history of allergy, hypersensitivity, or hypersensitivity reactions to iodinated contrast agents and always have emergency resuscitation equipment and trained personnel available prior to Iomeron administration. Monitor all patients for hypersensitivity reactions.
- Use the lowest necessary dose of Iomeron (iomeprol) in patients with renal impairment or with congestive heart failure.
- Avoid angiocardiography whenever possible in patients with homocystinuria because of the risk of inducing thrombosis and embolism.
- Thyroid storm has occurred after the intravascular use of iodinated contrast agents in patients with hyperthyroidism, or with an autonomously functioning thyroid nodule. Evaluate the risk in such patients before use of any iodinated contrast agent.
- Administer iodinated contrast agents with extreme caution in patients with known or suspected pheochromocytoma. Inject the minimum amount of contrast necessary, assess the blood pressure throughout the procedure, and have measures for treatment of a hypertensive crisis readily available.
- Severe cutaneous adverse reaction severity may increase and time to onset may decrease with repeat administration of contrast agents; prophylactic medications may not prevent or mitigate severe cutaneous adverse reactions. Avoid administering Iomeron to patients with a history of a severe cutaneous adverse reaction to Iomeron.
- Stop metformin at the time of, or prior to, Iomeron (Iomeron) administration in patients with an eGFR between 30 and 60 mL/min/1.73 m2; in patients with a history of hepatic impairment, alcoholism or heart failure; or in patients who will be administered intra-arterial iodinated contrast. Re-evaluate eGFR 48 hours after the imaging procedure and reinstitute metformin only after renal function is stable.
- Administration of iodinated contrast agents may interfere with thyroid uptake of radioactive iodine (I-131 and I-123) and decrease therapeutic and diagnostic efficacy in patients with carcinoma of the thyroid. The decrease in efficacy lasts for 6 to 8 weeks.
- Renal toxicity has been reported in a few patients with liver dysfunction who were given an oral cholecystographic agent followed by intravascular iodinated contrast agents. Administration of any intravascular iodinated contrast agent should therefore be postponed in patients who have recently received a cholecystographic contrast agent.

The Iomeron (iomeprol) barcode may not register accurately on U.S. barcode scanning systems. Institutions should manually input the product into their systems and confirm that their systems do not provide incorrect information when the product is scanned. Alternative procedures should be followed to assure that the correct drug product is being used and administered to individual patients.

To place an order for Iomeron (iomeprol), please contact Bracco Customer Service at 1-877-272-2269 or at Bracco.otc@diag.bracco.com. Hours of operation: Monday-Friday 8:30 AM – 6:00 PM EDT, excluding holidays.

To report adverse events associated with the use of this product, please contact Bracco Drug Safety at 1-800-257-5181, option 1, or at adverse.events@diag.bracco.com.

To report quality problems, or if you have any questions about the information contained in this letter or the use of Iomeron (iomeprol), please contact Bracco Professional Services at 1-800-257-5181, option 2, or at services.professional@diag.bracco.com.

Adverse reactions or quality problems experienced with the use of this product may be reported to the FDA's MedWatch Adverse Event Reporting program either online, by regular mail or by fax.

- Complete and submit the report Online: www.fda.gov/medwatch/report.htm
- Regular Mail or Fax: Download form www.fda.gov/MedWatch/getforms.htm or call 1-800-332-1088 to request a reporting form, then complete and return to the address on the pre-addressed form, or submit by fax to 1-800-FDA-0178 (1-800-332-0178)

Sincerely,

Alberto Spinazzi, MD
Senior Vice President
Chief Medical and Regulatory Officer
Bracco Group

Attachments:
Iomeron (iomeprol) U.K. SmPCs
Images of Iomeron (iomeprol) U.K. Bottle and Box Labels

Appendix 1. Comparisons of approved uses for iodinated contrast media in shortage and those manufactured by Bracco.

Table of Approved Intra-arterial Uses for Iodinated Contrast Media in Shortage, and for Those Manufactured by Bracco
POPULATION/ INDICATION | OMNIPAQUE (iohexol) mg iodine/mL | VISIPAQUE (iodixanol) mg iodine/mL | ULTRAVIST (iopromide) mg iodine/mL | ISOVUE (iopamidol) mg iodine/mL | IOMERON* (iomeprol) mg iodine/mL
ADULTS
Intra-arterial digital subtraction angiography | 140 | 270, 320 |  |  | 250, 300
Aortography | 300, 350 |  | 370 |  | 350, 400
Angiocardiography | 350 | 320 | 370 | 370 | 300, 350, 400
Visceral arteriography | 300, 350 | 320 | 370 | 370 | 300, 350, 400
Cerebral arteriography | 300 | 320 | 300 | 300 | 250, 300
Peripheral arteriography | 300, 350 | 320 | 300 | 300 | 300, 350, 400
*Approved uses for Iomeron (iomeprol) are from the U.K.

Table of Approved Intravenous Uses for Iodinated Contrast Media in Shortage, and for Those Manufactured by Bracco
POPULATION/ INDICATION | OMNIPAQUE (iohexol) mg iodine/mL | VISIPAQUE (iodixanol) mg iodine/mL | ULTRAVIST (iopromide) mg iodine/mL | ISOVUE (iopamidol) mg iodine/mL | IOMERON* (iomeprol) mg iodine/mL
ADULTS
CT head | 240, 300, 350 | 270, 320 | 300, 370 | 250, 300 | 250, 300, 350
CT body | 300, 350 | 270, 320 | 300, 370 | 250, 300 | 250, 300, 350, 400
Intravenous digital subtraction angiography | 350 |  |  |  | 250, 300, 350, 400
Peripheral venography | 240, 300 | 270 |  | 200 | 250, 300, 350
Excretory urography | 300, 350 | 270, 320 | 300 | 250, 300, 370 | 250, 300, 350, 400
*Approved uses for Iomeron (iomeprol) are from the U.K.

Appendix 2. Iomeron (iomeprol injection) adult dosing recommendations per U.K. Summary of Product Characteristics.

Table of adult dosing recommendations for Iomeron 250 single dose
(* Repeat as necessary)
Venography |  | 10 – 100 mL* maximum 250 mL 10 – 50 mL upper extremity 50 – 100 mL lower extremity
Cerebral arteriography |  | 5 – 12 mL*
Digital subtraction angiography
 | Intra arterial
 | visceral | 2 – 20 mL per artery* aorta 25-50 mL* both 250 mL maximum
 | peripheral | 5 – 10 mL per artery* maximum 250 mL
 | Intravenous | 30 – 60 mL* maximum 250 mL
Computed tomography
 | brain | 50 – 150 mL
 | body | 40 – 150 mL maximum 250 mL
Urography intravenous |  | 50 – 150 mL

Table of adult dosing recommendations for Iomeron 300 single dose
(* Repeat as necessary)
Peripheral arteriography |  | 10 – 90 mL*
Venography |  | 10 – 100 mL* maximum 250 mL 10 – 50 mL upper extremity 50 – 100 mL lower extremity
Angiocardiography and left ventriculography |  | 30 – 80 mL maximum 250 mL
Cerebral arteriography |  | 5 – 12 mL*
Visceral arteriography |  | 5 – 50 mL* or according to type of examination; maximum 250 mL
Digital subtraction angiography
 | Intra arterial
 | visceral | 2 – 20 mL per artery* aorta 25-50 mL* both 250 mL maximum
 | peripheral | 5 – 10 mL per artery* maximum 250 mL
 | Intravenous | 30 – 60 mL* maximum 250 mL
Computed tomography
 | brain | 50 – 150 mL
 | body | 40 – 150 mL maximum 250 mL
Urography intravenous |  | 50 – 150 mL

Table of adult dosing recommendations for Iomeron 300 multidose
(* Repeat as necessary)

Computed tomography

brain

50 – 150 mL

body

40 – 150 mL
maximum 250 mL

Table of adult dosing recommendations for Iomeron 350 single dose
(* Repeat as necessary)
Peripheral arteriography |  | 10 – 90 mL*
Venography |  | 10 – 100 mL* maximum 250 mL 10 – 50 mL upper extremity 50 – 100 mL lower extremity
Aortography |  | 50 – 80 mL
Angiocardiography and left ventriculography |  | 30 – 80 mL maximum 250 mL
Coronary arteriography |  | 4 – 10 mL per artery*
Visceral arteriography |  | 5 – 50 mL* or according to type of examination; maximum 250 mL
Intravenous digital subtraction angiography |  | 30 – 60 mL* maximum 250 mL
Computed tomography
 | brain | 50 – 150 mL
 | body | 40 – 150 mL maximum 250 mL
Urography intravenous |  | 50 – 150 mL

Table of adult dosing recommendations for Iomeron 350 multidose
(* Repeat as necessary)

Computed tomography

brain

50 – 150 ml

body

40 – 150 ml
maximum 250 mL

Table of adult dosing recommendations for Iomeron 400 single dose
(* Repeat as necessary)
Peripheral arteriography |  | 10 – 90 mL*
Aortography |  | 50 – 80 mL
Angiocardiography and left ventriculography |  | 30 – 80 mL maximum 250 mL
Coronary arteriography |  | 4 – 10 mL per artery*
Visceral arteriography |  | 5 – 50 mL* or according to type of examination
Intravenous digital subtraction angiography |  | 30 – 60 mL* maximum 250 mL
Computed tomography of the body |  | 40 – 150 mL maximum 250 mL
Urography intravenous |  | 50 – 150 mL

Table of adult dosing recommendations for Iomeron 400 multidose
(* Repeat as necessary)

Computed tomography of the body

40 – 150 mL
maximum 250 mL

UK Iomeron Vial and Carton Labels

Product Description | Iodine Concentration (mg iodine/mL) | Fill Volume | Vial Label | Carton Label
Iomeron (iomeprol injection) 250 | 250 | 100 mL
Iomeron (iomeprol injection) 300 | 300 | 100 mL
Iomeron (iomeprol injection) 300 | 300 | 200 mL
Iomeron (iomeprol injection) 300 | 300 | 500 mL
Iomeron (iomeprol injection) 350 | 350 | 100 mL
Iomeron (iomeprol injection) 350 | 350 | 200 mL
Iomeron (iomeprol injection) 350 | 350 | 500 mL
Iomeron (iomeprol injection) 400 | 400 | 100 mL
Iomeron (iomeprol injection) 400 | 400 | 200 mL
Iomeron (iomeprol injection) 400 | 400 | 500 mL

MEDICATION GUIDE

1. NAME OF THE MEDICINAL PRODUCT

Iomeron 250, solution for injection

2. QUALITATIVE AND QUANTITATIVE COMPOSITION

Contains 51.03% w/v of iomeprol equivalent to 25% iodine or 250mg iodine/ml.

For the full list of excipients, see section 6.1.

3. PHARMACEUTICAL FORM

Solution for injection.

4. CLINICAL PARTICULARS

4.1 Therapeutic indications

X-ray contrast medium used for:

- venography
- cerebral arteriography
- digital subtraction angiography
- computed tomography enhancement
- urography
- cavernosography
- myelography

4.2 Posology and method of administration

venography
venography |  | adults | 10 - 100ml*
venography |  |  | max 250ml
venography |  |  | 10 - 50ml upper extremity
venography |  |  | 50 - 100 lower extremity
cerebral arteriography
cerebral arteriography |  | adults | 5 - 12ml*
cerebral arteriography |  | children | 3 - 7ml or * *
digital subtraction angiography
 | Intra arterial
 | visceral | adults | 2 - 20ml per artery*
 |  |  | aorta 25-50ml*
 |  |  | both 250ml max
 | peripheral | adults | 5 - 10ml per artery*
 |  |  | max 250ml
 | intravenous | adults | 30 - 60ml*
 |  |  | max 250ml
computed tomography
 | brain | adults | 50 - 150
 |  | children | * *
 | body | adults | 40 - 150ml
 |  |  | max 250ml
 |  | children | * *
 | urography | adults | 50 - 150ml
 | intravenous
 |  | neonates | 3 - 4.8ml/kg
 |  | babies | 2.5 - 4ml/kg
 |  | children | 1 - 2.5ml/kg or *
 | cavernosography | adults | 40 - 250ml
 | myelography | adults | 12 - 18ml
 |  |  | by lumbar injection
* Repeat as necessary
* * According to body size and age

In elderly patients the lowest effective dose should be used.

Unless otherwise instructed by the doctor, a normal diet may be maintained on the day of the examination.

In myelography, lower doses may be used for lumbar or thoracic studies and higher doses for cervical or total columnar studies. Regardless of the nature of the myelographic study, Iomeron should be injected slowly over 1-2 minutes.

The X ray can be taken up to 60 minutes following injection. Post myelographic CT of the spinal column should be delayed for approximately four hours to allow dilution and clearance of excessive contrast.

4.3 Contraindications

Hypersensitivity to the active substance or any of the excipients.
Intrathecal concomitant administration of corticosteroids with contrast media is contraindicated.

4.4 Special warnings and special precautions for use

In consideration of possible complications, the patient should be kept under observation for at least 30 minutes after the examination.

Extreme caution during injection of contrast media is necessary to avoid extravasation.

Hydration
Patients must be well hydrated, and any relevant abnormalities of fluid or electrolyte balance should be corrected prior to and following contrast media injection. Especially patients with diabetes mellitus, polyuria, oligouria, hyperuricaemia, infants, small children, and elderly patients, should not be exposed to dehydration. Also patients with severely compromised hepatic and renal impairment are more at risk. Caution should be exercised in hydrating patients with underlying conditions that may be worsened by fluid overload, including congestive heart failure.

Rehydration prior to use of iomeprol is recommended in patients with sickle cell disease.

Special population
Hypersensitivity to iodinated contrast media, allergic predisposition

A positive history of allergy, asthma or untoward reaction during previous similar investigations indicates a need for extra caution since, as with other contrast media, this product may provoke anaphylaxis or other manifestations of allergy with nausea, vomiting, dyspnoea, erythema, urticaria and hypotension. The benefits should clearly outweigh the risks in such patients and appropriate resuscitative measures should be immediately available. The primary treatments are as follows:

Effect | Major Symptoms | Primary Treatment
Vasomotor effect | warmth nausea/vomiting | reassurance
Cutaneous | scattered hives severe urticaria | H1-antihistamines H2-antihistamines
Bronchospastic | wheezing | oxygen Beta-2-agonist inhalers
Anaphylactoid | angioedema | oxygen
reaction | urticaria bronchospasm hypotension | iv fluids adrenergics (iv epinephrine) Inhaled beta-2-adrenergics
 |  | antihistamines (H1-and H2- blockers) corticosteroids
Hypotensive | hypotension | iv fluids
Vagal reaction | hypotension bradycardia | iv fluids iv atropine

From: Bush WH; The Contrast Media Manual; Katzburg RW Ed.; Williams and Wilkins; Baltimore 1992; Chapter 2 p 23

The risk of bronchospasm-inducing reactions in asthmatic patients is higher after contrast media administration, especially in patients taking beta-blockers.

Hypersensitivity testing
In patients with suspected or known hypersensitivity to contrast media, sensitivity test doses are not recommended, as severe or fatal reactions to contrast media are not predictable from sensitivity test.

Myelomatosis or paraproteinaemias are conditions predisposing to renal impairment following CM administration. The benefits of the use of a contrast-enhanced procedure should be carefully weighted against the possible risk. Adequate hydration and monitoring of renal function are recommended after CM administration.

Cardiovascular diseases
Care should be taken in severe cardiac disease particularly heart failure and coronary artery disease. Reactions may include pulmonary oedema, haemodynamic changes, ischaemic ECG changes and arrhythmias. In severe, chronic hypertension the risk of renal damage following administration of a contrast medium is increased. In these cases the risks associated with the catheterization procedure are increased.

The product should be used with caution in patients with hyperthyroidism or goitre. Use may interfere with thyroid function tests.

The administration of iodinated contrast media may aggravate myasthenia signs and symptoms.

CNS Disorders
Particular care is needed in patients with acute cerebral infarction, acute intracranial haemorrhage and any conditions involving damage to the blood brain barrier, brain oedema or acute demyelination. Convulsive seizures are more likely in patients with intracranial tumours or metastases or with a history of epilepsy.

Neurological symptoms related to cerebrovascular diseases, intracranial tumours/metastases or degenerative or inflammatory pathologies may be exacerbated.

There is an increased risk of transient neurological complications in patients with symptomatic cerebrovascular disease e.g. stroke, transient ischaemic attacks. Cerebral ischaemic phenomena may be caused by intravascular injection.

Anticonvulsant therapy should not be discontinued.

In acute and chronic alcoholism the increase in blood brain barrier permeability facilitates the passage of the contrast medium into cerebral tissue possibly leading to CNS disorders. There is a possibility of a reduced seizure threshold in alcoholics.

In patients with a drug addiction there is also the possibility of a reduced seizure threshold.

Patients with phaeochromocytoma may develop severe, occasionally uncontrollable hypertensive crises during intra-arterial administration. Premedication with an alpha and beta receptor blocker is recommended in these patients. Pronounced excitement, anxiety and pain can cause side effects or intensify reaction to the contrast medium. A sedative may be given.

Renal impairment
In patients with moderate to severe impairment of renal function, attention should be paid to renal function parameters before re-examining the patient with a contrast media.
Preventive measures include:

- identification of high-risk patients;
- ensuring adequate hydration before CM administration, preferably by maintaining i.v. infusion before and during the procedure and until the CM has been cleared by the kidneys;

avoiding whenever possible, the administration of nephrotoxic drugs or major surgery or procedure such as renal angioplasty, until the CM has been cleared;

A combination of severe hepatic and renal impairment delays excretion of the contrast medium therefore such patients should not be examined unless absolutely necessary.

Diabetes mellitus
Care should be taken in renal impairment and diabetes. In these patients it is important to maintain hydration in order to minimise deterioration in renal function.
The presence of renal damage in diabetic patients is one of the factors predisposing to renal impairment following contrast media administration. This may precipitate lactic acidosis in patients who are taking metformin (see section 4.5 - Interaction with medicaments and other forms of interaction).

Children: Infants up to 1 year, especially the new-born, are particularly susceptible to electrolyte imbalance and haemodynamic alterations. Care should be taken regarding the dosage used.

Transient hypothyroidism may occur in neonates when the mother or the neonate has received an iodinated contrast agent. Thyroid function tests (usually TSH and T4) are recommended in neonates 7-10 days and 1 month after exposure to Iomeron especially in preterm neonates.

Elderly: There is special risk of reactions involving the circulatory system such that myocardial ischaemia, major arrhythmias and extrasystoles are more likely to occur. A combination of neurological disturbances and vascular pathologies present a serious complication. The probability of acute renal insufficiencies is higher in these people.

Precautions for dedicated exams

Angiography
Non ionic contrast media have less antiocoagulant activity in vitro than ionic media. Meticulous attention should therefore be paid to angiographic technique. Non ionic media should not be allowed to remain in contact with blood in a syringe, and intravascular catheters should be flushed frequently to minimise the risk of clotting which, rarely, has led to serious thromboembolic complications.

Intravascular administration should be performed if possible with the patient lying down. The patient should be kept in this position and closely observed for at least 30 minutes after the procedure since the majority of severe incidents occur with this time.

Myelography
Following intrathecal use, the patient should rest with the head and the chest elevated for 1 hour and be kept well hydrated. Thereafter, he/she may ambulate carefully, but bending down must be avoided. If remaining in bed, the head and chest should be kept elevated for 6 hours. Patients, suspected of having a lower seizure threshold should be observed during this period.

Venography
Special care is required when venography is performed in patients with thrombosis, phlebitis, severe ischaemic disease, local infection or a totally obstructed artero-venous system.

4.5 Interaction with other medicinal products and other forms of interaction

Use of the product may interfere with tests for thyroid function. Vasopressor agents should not be administered prior to iomeprol.

Treatment with drugs that lower the seizure threshold such as certain neuroleptics (MAO inhibitors, tricyclic antidepressants), analeptics, and anti-emetics and phenotiazine derivatives should be discontinued 48 hours before the examination. Treatment should not be resumed until 24 hours post-procedure.

It has been reported that cardiac and/or hypertensive patients under treatment with diuretics, ACE-inhibitors, and/or beta blocking agents are at higher risk of adverse reactions when administered iodinated contrast media.

Beta-blockers may impair the response to treatment of bronchospasm induced by contrast medium.

Patients with normal renal function can continue to take metformin normally. In diabetic patients with diabetic nephropathy, under treatment with metformin and with moderate renal impairment, metformin should be stopped at the time of, or prior to the procedure and withheld for 48 hours subsequent to the procedure and reinstituted only after renal function has been re-evaluated and found to be normal In emergency patients in whom renal function is either impaired or unknown, the physician shall weigh out risk and benefit of an examination with a contrast medium and take precautions. Metformin should be stopped from time of contrast medium administration. After the procedure the patient should be monitored for signs of lactic acidosis. Metformin should be restarted 48 hours after contrast medium if serum creatinine/eGFR is unchanged from the pre-imaging level.

Allergy-like reactions to contrast media are more frequent and may manifest as delayed reactions in patients treated with immuno-modulators, like Interleukin-2 (IL-2).

Epidural and intrathecal corticosteroids should never be concurrently administered when iodinated contrast media are used, because corticosteroids may promote and affect the signs and symptoms of arachnoiditis (see section 4.3 - Contraindications).

4.6 Fertility, pregnancy and lactation

Women of childbearing potential
Appropriate investigations and measures should be taken when exposing women of child-bearing potential to any X-ray examination, whether with or without contrast medium.

Pregnancy
Animal studies have not indicated any harmful effects with respect to the course of pregnancy or on the health of the unborn or neonate. The safety of iomeprol in human pregnancy however has not been established. Therefore avoid in pregnancy unless there is no safer alternative. Since, wherever possible, exposure to radiation should be avoided during pregnancy, the benefits of any X ray examination, whether with or without contrast material, should for this reason alone be carefully weighed against the possible risk.

Breastfeeding
No human data exist concerning the excretion of iomeprol in breast milk. Animal studies have demonstrated that the excretion of iomeprol in breast milk is similar to that of other contrast agents and that these compounds are only minimally absorbed by the gastrointestinal tract of the young. Adverse effects on the nursing infant are therefore unlikely to occur.

Stopping breastfeeding is unnecessary.

4.7 Effects on ability to drive and use machines

There is no known effect on the ability to drive and operate machines.

After intrathecal administration, it is recommended that the patient should wait 24 hours before driving or operating machinery.

4.8 Undesirable effects

General

The use of iodinated contrast media may cause untoward side effects. They are usually mild to moderate and transient in nature. However, severe and life-threatening reactions sometimes leading to death have been reported. In most cases, reactions occur within minutes of dosing but at times reactions may occur at later time.

Anaphylaxis (anaphylactoid/hypersensitivity reactions) may manifest with various symptoms, and rarely does any one patient develop all the symptoms. Typically, in 1 to 15 min (but rarely after as long as 2 h), the patient complains of feeling abnormal, agitation, flushing, feeling hot, sweating increased, dizziness, increased lacrimation, rhinitis, palpitations, paresthesia, pruritus, sore throat and throat tightness, dysphagia, cough, sneezing, urticaria, erythema, mild localised oedema, angioneurotic oedema and dyspnoea due to glottic/laryngeal/pharyngeal oedema and/or spasm manifesting with wheezing, and bronchospasm.
Nausea, vomiting, abdominal pain, and diarrhoea are also reported.
These reactions, which can occur independently of the dose administered or the route of administration, may represent the first signs of circulatory collapse.
Administration of the contrast medium must be discontinued immediately and, if needed, appropriate specific treatment urgently initiated via venous access.
Severe reactions involving the cardiovascular system, such as vasodilatation, with pronounced hypotension, tachycardia, dyspnoea, agitation, cyanosis and loss of consciousness progressing to respiratory and/or cardiac arrest may result in death. These events can occur rapidly and require full and aggressive cardio-pulmonary resuscitation.
Primary circulatory collapse can occur as the only and/or initial presentation without respiratory symptoms or without other signs or symptoms outlined above.

The adverse reactions reported in clinical trials among 4,903 adult patients and from post-marketing surveillance are represented in the tables below by frequency and classified by MedDRA system organ class.

Within each frequency grouping, adverse reactions are presented in order of decreasing seriousness.

4.8.1 Intravascular administration

Adult patients involved in clinical trials with intravascular administration of Iomeprol were 4,515.

Adults
System Organ Class | Adverse Reactions
System Organ Class | Clinical Trials |  |  | Post-marketing Surveillance
System Organ Class | Common (≥1/100 t o <1/10) | Uncommon (≥1/1000 to <1/100) | Rare (≥1/10,000 to <1/1000) | Frequency unknown*
Blood and lymphatic system disorders |  |  |  | Thrombocytopenia, Haemolytic anaemia
Immune system disorders |  |  |  | Anaphylactoid reaction
Psychiatric disorders |  |  |  | Anxiety Confusional state
Nervous system disorders |  | Headache Dizziness | Presyncope | Coma Transient ischaemic attack Paralysis Syncope Convulsion Loss of consciousness Dysarthria Paraesthesia Amnesia Somnolence Taste abnormality
Eye disorders |  |  |  | Blindness transient Visual disturbance Conjunctivitis Lacrimation increased Photopsia
Cardiac disorders |  |  | Bradycardia Tachycardia Extrasystoles | Cardiac arrest Myocardial infarction Cardiac failure Angina pectoris Arrhythmia Ventricular or atrial fibrillation Atrioventricular block Palpitations Cyanosis
Vascular disorders |  | Hypertension | Hypotension | Circulatory collapse or shock Hot flush Flushing Pallor
Respiratory, thoracic and mediastinal disorders |  | Dyspnoea |  | Respiratory arrest Acute respiratory distress syndrome (ARDS) Pulmonary oedema Laryngeal oedema Pharyngeal oedema Bronchospasm Asthma Cough Hyperventilation Pharynx discomfort Laryngeal discomfort Rhinitis Dysphonia
Gastrointestinal disorders |  | Nausea Vomiting |  | Diarrhoea Abdominal pain Salivary hypersecretion Dysphagia Salivary gland enlargement
Skin and subcutaneous tissue disorders |  | Erythema Urticaria Pruritus | Rash | Acute generalized exanthematous pustulosis Angioedema Cold sweat Sweating increased
Musculoskeletal and connective tissue disorder |  |  | Back pain | Arthralgia
Renal and urinary disorders |  |  |  | Renal failure
General disorders and administration site conditions | Feeling hot | Chest pain Injection site warmth and pain | Asthenia Rigors Pyrexia | Injection site reaction** Coldness local Fatigue Malaise Thirst
Investigations |  |  | Blood creatinine increased | Electrocardiogram ST segment elevation Electrocardiogram abnormal
* Since the reactions were not observed during clinical trials with 4515 patients, best estimate is that their relative occurrence is rare (≥1/10,000 to <1/1000).
The most appropriate MedDRA term is used to describe a certain reaction and its symptoms and related conditions.
** Injection site reactions comprise injection site pain and swelling. In the majority of cases they are due to extravasation of contrast medium. These reactions are usually transient and result in recovery without sequelae. Cases of extravasation with inflammation, skin necrosis and even development of compartment syndrome have been reported.

Coronary artery thrombosis and coronary artery embolism have been reported as a complication of coronary catheterization procedures.

Vasospasm and consequent ischaemia have been observed during intra-arterial injections of contrast medium, in particular after coronary and cerebral angiography often procedurally related and possibly triggered by the tip of the catheter or excess catheter pressure.

As with other iodinated contrast media, very rare cases of mucocutaneous syndromes, including Stevens-Johnson syndrome, toxic epidermal necrolysis (Lyell syndrome) and erythema multiforme, have been reported following the administration of Iomeprol injection.

Paediatric patients

There is limited experience with paediatric patients. The clinical trial paediatric safety database comprises 167 patients.

The Iomeprol safety profile is similar in children and adults.

4.8.2 Intrathecal administration

Adults

Adults patients involved in clinical trials with intrathecal administration of Iomeprol were 388.

The most frequently reported adverse reactions following intrathecal administration of Iomeprol are headache, dizziness, nausea, vomiting and back pain. These reactions are usually mild to moderate and transient in nature. Rarely, headache may persist for days. Most side effects occur some hours (3 to 6 hours) after the procedure, due to the distribution of the contrast medium in the CSF circulation from the site of administration to the intravascular space (see section 5.2: Pharmacokinetic properties). Most reactions usually occur within 24 hours after injection.

System Organ Class | Adverse Reactions
System Organ Class | Clinical Trials |  |  | Post-marketing Surveillance
System Organ Class | Very common (≥1/10) | Common (≥1/100 to <1/10) | Uncommon (≥1/1000 to <1/100) | Frequency unknown*
Immune system disorders |  |  |  | Anaphylactoid reaction
Nervous system disorders | Headache | Dizziness | Hypoaesthesia Paraesthesia Paraparesis Loss of consciousness Somnolence | Epilepsy
Vascular disorders |  | Hypertension | Hypotension Flushing
Gastrointestinal disorders |  | Nausea Vomiting
Skin and subcutaneous tissue disorders |  |  | Hyperhidrosis Pruritus | Rash
Musculoskeletal and connective tissue disorder |  | Back pain Pain in extremity | Musculoskeletal stiffness Neck pain
General disorders and administration site conditions |  | Injection site reaction** | Feeling hot Pyrexia
* Since the reactions were not observed during clinical trials with 388 patients, best estimate is that their relative occurrence is uncommon (≥ 1/1000 to <1/100.
The most appropriate MedDRA term is used to describe a certain reaction and its symptoms and related conditions.
** Injection site reactions comprise application site pain, injection site discomfort, injection site pain and injection site warmth.

Paediatric patients

No adverse reactions were reported after intrathecal administration of Iomeprol both in clinical trials and in the post-marketing surveillance.

4.8.3 Administration to body cavities

After injection of an iodinated contrast media in body cavities, contrast media are slowly absorbed from the area of administration into the systemic circulation and subsequently cleared by renal elimination.

Blood amylase increased is common following ERCP. Very rare cases of pancreatitis have been described.

The reactions reported in cases of arthrography and fistulography usually represent irritative manifestations superimposed on pre-existing conditions of tissue inflammation.

Hypersensitivity reactions are rare, generally mild and in the form of skin reactions. However, the possibility of severe anaphylactoid reactions cannot be excluded.

As with other iodinated contrast media, pelvic pain and malaise may occur after hysterosalpingography.

Reporting of suspected adverse reactions
Reporting suspected adverse reactions after authorisation of the medicinal product is important. It allows continued monitoring of the benefit/risk balance of the medicinal product. Healthcare professionals are asked to report any suspected adverse reactions via the Yellow Card Scheme
Website: www.mhra.gov.uk/yellowcard or search for MHRA Yellow Card in the Google Play or Apple App Store.

4.9 Overdose

The effects of overdose on the pulmonary and cardiovascular systems may become life-threatening. Treatment consists of support of the vital functions and prompt use of symptomatic therapy. Iomeprol does not bind to plasma or serum proteins and is therefore dialyzable.

5 PHARMACOLOGICAL PROPERTIES

5.1 Pharmacodynamic properties

ATC code: V08AB10

Iomeprol is a low osmolality, non-ionic organic molecule with radio-opacity conferred by an iodine content of 49% of the molecular weight. It is formulated for use as an intravascular/intracavitary/ intrathecal contrast medium in concentrations of up to 400mg iodine per ml. Even at this concentration the low viscosity allows delivery of high doses through thin catheters.

5.2 Pharmacokinetic properties

The pharmacokinetics of intravascularly administered iomeprol are similar to those of other iodinated contrast media and conform to a two-compartment model with a rapid distribution and a slower elimination phase. In healthy subjects, the mean distribution and elimination half-lives of iomeprol were 0.5 hours and 1.9 hours respectively.

Distribution volume is similar to that of extra cellular fluid. There is no significant serum protein binding and iomeprol is not metabolized.

Elimination is almost exclusively through the kidneys (90% of the dose recovered in the urine within 96 hours of its administration) and is rapid (50% of an intravascularly administered dose within 2 hours).

Following intrathecal administration to animals, iomeprol is completely cleared from the CSF and passes into the plasma compartment.

5.3 Preclinical Safety Data

Pre-clinical data reveal no special hazard for humans based on conventional studies of safety pharmacology, repeated dose toxicity, genotoxicity, toxicity to reproduction.

Results from studies in rats, mice and dogs demonstrate that iomeprol has an acute intravenous or intra-arterial toxicity similar to that of the other non ionic contrast media, as well as a good systemic tolerability after repeated intravenous administrations in rats and dogs.

6. PHARMACEUTICAL PARTICULARS

6.1 List of excipients

trometamol
hydrochloric acid
water for injection

6.2 Incompatibilities

In the absence of compatibility studies, this medicinal product must not be mixed with other medicinal products.

6.3 Shelf Life

Five years

6.4 Special precautions for storage

Store below 30°C
Protect from light

6.5 Nature and contents of containers

Colourless Type I or Type II glass bottles with rubber/aluminium cap.
Quantities of 20, 30, 50, 75, 100, 150, 200 or 250 ml of solution.

6.6 Special precautions for disposal and other handling

Bottles containing contrast media solution are not intended for the withdrawal of multiple doses. The rubber stopper should never be pierced more than once. The use of proper withdrawal cannulas for piercing the stopper and drawing up the contrast medium is recommended.
Before use, examine the product to assure that the container and closure have not been damaged. Do not use the solution if it is discolored or particulate matter is present.

The contrast medium should not be drawn into the syringe until immediately before use. Withdrawal of contrast agents from their containers should be accomplished under aseptic conditions with sterile syringes. Sterile techniques must be used with any spinal puncture or intravascular injection, and with catheters and guidewires. If non-disposable equipment is used, scrupulous care should be taken to prevent residual contamination with traces of cleansing agents.

It is desirable that solutions of contrast media for intravascular and intrathecal use should be at body temperature when injected.

Any residue of contrast medium in the syringe must be discarded. Solutions not used in one examination session or waste material, such as the connecting tubes, should be disposed in accordance with local requirements.

7. MARKETING AUTHORISATION HOLDER

Bracco UK Ltd
Magdalen Centre
The Oxford Science Park
Oxford, OX4 4GA
United Kingdom

8. MARKETING AUTHORISATION NUMBER

18920/0003

9. DATE OF FIRST AUTHORISATION/RENEWAL OF AUTHORISATION

11 December 1992 / 29 December 1998

10. DATE OF REVISION OF THE TEXT

19 January 2022

MEDICATION GUIDE

1. NAME OF THE MEDICINAL PRODUCT

Iomeron 300, solution for injection

2. QUALITATIVE AND QUANTITATIVE COMPOSITION

Contains 61.24% w/v of iomeprol equivalent to 30% iodine or 300mg iodine/ml.

For the full list of excipients, see section 6.1.

3. PHARMACEUTICAL FORM

Solution for injection.

4. CLINICAL PARTICULARS

4.1 Therapeutic indications

X-ray contrast medium used for:

- peripheral arteriography
- venography
- angiocardiography and left ventriculography
- cerebral arteriography
- visceral arteriography
- digital subtraction angiography
- computed tomography enhancement
- urography
- ERCP
- dacryocystography
- sialography
- fistulography
- galactography
- myelography

4.2 Posology and method of administration

peripheral arteriography |  | adults children | 10 - 90ml * * *
venography |  | adults | 10 - 100ml* max 250ml 10 - 50ml upper extremity 50 - 100 lower extremity
angiocardiography and left ventriculography |  | adults | 30 - 80ml max 250ml
 |  | children | * *
cerebral arteriography |  | adults | 5 - 12ml*
 |  | children | 3 - 7ml or * *
visceral arteriography |  | adults | 5 - 50ml* or according to type of examination; max 250ml
 |  | children | * *
digital subtraction angiography
 | Intra arterial
 | visceral | adults | 2 - 20ml per artery* aorta 25-50ml* both 250ml max
 | peripheral | adults | 5 - 10ml per artery* max 250ml
 | intravenous | adults | 30 - 60ml* max 250ml
computed tomography
 | brain | adults | 50 - 150ml
 |  | children | * *
 | body | adults | 40 - 150ml max 250ml
 |  | children | * *
 | urography intravenous | adults | 50 - 150ml
 |  | neonates | 3 - 4.8ml/kg
 |  | babies | 2.5 - 4ml
 |  | children | 1 - 2.5ml/kg or *
 | arthrography | adults | 1 - 10ml
 | ERCP | adults | 12 - 30ml
 | dacryocystography | adults | 3 - 8ml
 | sialography | adults | 1 - 3ml
 | fistulography | adults | 1 - 50ml
 | galactography | adults | 0.2 - 1.5ml
 | myelography | adults | 10 - 15ml by lumbar injection
* Repeat as necessary
* * According to body size and age

In elderly patients the lowest effective dose should be used.

Unless otherwise instructed by the doctor, a normal diet may be maintained on the day of the examination.

In myelography, lower doses may be used for lumbar or thoracic studies and higher doses for cervical or total columnar studies. Regardless of the nature of the myelographic study, Iomeron should be injected slowly over 1-2 minutes.

The X ray can be taken up to 60 minutes following injection. Post myelographic CT of the spinal column should be delayed for approximately four hours to allow dilution and clearance of excessive contrast.

4.3 Contraindications

Hypersensitivity to the active substance or any of the excipients.
Intrathecal concomitant administration of corticosteroids with contrast media is contraindicated.

4.4 Special warnings and special precautions for use

In consideration of possible complications, the patient should be kept under observation for at least 30 minutes after the examination.

Extreme caution during injection of contrast media is necessary to avoid extravasation.

Hydration
Patients must be well hydrated, and any relevant abnormalities of fluid or electrolyte balance should be corrected prior to and following contrast media injection. Especially patients with diabetes mellitus, polyuria, oligouria, hyperuricaemia, infants, small children, and elderly patients, should not be exposed to dehydration. Also patients with severely compromised hepatic and renal impairment are more at risk. Caution should be exercised in hydrating patients with underlying conditions that may be worsened by fluid overload, including congestive heart failure.

Rehydration prior to use of iomeprol is recommended in patients with sickle cell disease.

Special population
Hypersensitivity to iodinated contrast media, allergic predisposition
A positive history of allergy, asthma or untoward reaction during previous similar investigations indicates a need for extra caution since, as with other contrast media, this product may provoke anaphylaxis or other manifestations of allergy with nausea, vomiting, dyspnoea, erythema, urticaria and hypotension. The benefits should clearly outweigh the risks in such patients and appropriate resuscitative measures should be immediately available. The primary treatments are as follows:

Effect | Major Symptoms | Primary Treatment
Vasomotor effect | warmth nausea/vomiting | reassurance
Cutaneous | scattered hives severe urticaria | H1-antihistamines H2-antihistamines
Bronchospastic | wheezing | oxygen Beta-2-agonist inhalers
Anaphylactoid | angioedema | oxygen
reaction | urticaria bronchospasm hypotension | iv fluids adrenergics (iv epinephrine) Inhaled beta-2-adrenergics
 |  | antihistamines (H1-and H2- blockers) corticosteroids
Hypotensive | hypotension | iv fluids
Vagal reaction | hypotension bradycardia | iv fluids iv atropine

From: Bush WH; The Contrast Media Manual; Katzburg RW Ed.; Williams and Wilkins; Baltimore 1992; Chapter 2 p 23

The risk of bronchospasm-inducing reactions in asthmatic patients is higher after contrast media administration, especially in patients taking beta-blockers.

Hypersensitivity testing
In patients with suspected or known hypersensitivity to contrast media, sensitivity test doses are not recommended, as severe or fatal reactions to contrast media are not predictable from sensitivity test.

Myelomatosis or paraproteinaemias are conditions predisposing to renal impairment following CM administration. The benefits of the use of a contrast-enhanced procedure should be carefully weighted against the possible risk. Adequate hydration and monitoring of renal function are recommended after CM administration.

Cardiovascular diseases
Care should be taken in severe cardiac disease particularly heart failure and coronary artery disease. Reactions may include pulmonary oedema, haemodynamic changes, ischaemic ECG changes and arrhythmias.

In severe, chronic hypertension the risk of renal damage following administration of a contrast medium is increased. In these cases the risks associated with the catheterization procedure are increased.

The product should be used with caution in patients with hyperthyroidism or goitre. Use may interfere with thyroid function tests.

The administration of iodinated contrast media may aggravate myasthenia signs and symptoms.

CNS Disorders
Particular care is needed in patients with acute cerebral infarction, acute intracranial haemorrhage and any conditions involving damage to the blood brain barrier, brain oedema or acute demyelination. Convulsive seizures are more likely in patients with intracranial tumours or metastases or with a history of epilepsy.

Neurological symptoms related to cerebrovascular diseases, intracranial tumours/metastases or degenerative or inflammatory pathologies may be exacerbated.

There is an increased risk of transient neurological complications in patients with symptomatic cerebrovascular disease eg stroke, transient ischaemic attacks. Cerebral ischaemic phenomena may be caused by intravascular injection.

Anticonvulsant therapy should not be discontinued.

In acute and chronic alcoholism the increase in blood brain barrier permeability facilitates the passage of the contrast medium into cerebral tissue possibly leading to CMS disorders. There is a possibility of a reduced seizure threshold in alcoholics.

In patients with a drug addiction there is also the possibility of a reduced seizure threshold.

Patients with phaeochromocytoma may develop severe, occasionally uncontrollable hypertensive crises during intra-arterial administration. Premedication with an alpha and beta receptor blocker is recommended in these patients.

Pronounced excitement, anxiety and pain can cause side effects or intensify reaction to the contrast medium. A sedative may be given.

Renal impairment
In patients with moderate to severe impairment of renal function, attention should be paid to renal function parameters, in particular before re-examining the patient with a contrast media.
Preventive measures include:

- identification of high-risk patients;
- ensuring adequate hydration before CM administration, preferably by maintaining i.v. infusion before and during the procedure and until the CM has been cleared by the kidneys;

avoiding whenever possible, the administration of nephrotoxic drugs or major surgery or procedure such as renal angioplasty, until the CM has been cleared;

A combination of severe hepatic and renal impairment delays excretion of the contrast medium therefore such patients should not be examined unless absolutely necessary.

Diabetes mellitus
Care should be taken in renal impairment and diabetes. In these patients it is important to maintain hydration in order to minimise deterioration in renal function.
The presence of renal damage in diabetic patients is one of the factors predisposing to renal impairment following contrast media administration. This may precipitate lactic acidosis in patients who are taking metformin (see section 4.5 - Interaction with medicaments and other forms of interaction).

Children:
Infants up to 1 year, especially the new-born, are particularly susceptible to electrolyte imbalance and haemodynamic alterations. Care should be taken regarding the dosage used.

Transient hypothyroidism may occur in neonates when the mother or the neonate has received an iodinated contrast agent. Thyroid function tests (usually TSH and T4) are recommended in neonates 7-10 days and 1 month after exposure to Iomeron especially in preterm neonates.

Elderly:
There is special risk of reactions involving the circulatory system such that myocardial ischaemia, major arrhythmias and extrasystoles are more likely to occur. A combination of neurological disturbances and vascular pathologies present a serious complication. The probability of acute renal insufficiencies is higher in these people.

Precautions for dedicated exams

Angiography
Non ionic contrast media have less antiocoagulant activity in vitro than ionic media. Meticulous attention should therefore be paid to angiographic technique. Non ionic media should not be allowed to remain in contact with blood in a syringe, and intravascular catheters should be flushed frequently to minimise the risk of clotting which, rarely, has led to serious thromboembolic complications.

Intravascular administration should be performed if possible with the patient lying down. The patient should be kept in this position and closely observed for at least 30 minutes after the procedure since the majority of severe incidents occur with this time.

Myelography
Following intrathecal use, the patient should rest with the head and the chest elevated for 1 hour and be kept well hydrated. Thereafter, he/she may ambulate carefully, but bending down must be avoided. If remaining in bed, the head and chest should be kept elevated for 6 hours. Patients, suspected of having a lower seizure threshold should be observed during this period.

Venography
Special care is required when venography is performed in patients with thrombosis, phlebitis, severe ischaemic disease, local infection or a totally obstructed artero-venous system.

4.5 Interaction with other medicaments and other forms of interaction

Use of the product may interfere with tests for thyroid function. Vasopressor agents should not be administered prior to iomeprol.

Treatment with drugs that lower the seizure threshold such as certain neuroleptics (MAO inhibitors, tricyclic antidepressants), analeptics, and anti-emetics and phenotiazine derivatives should be discontinued 48 hours before the examination. Treatment should not be resumed until 24 hours post-procedure.

It has been reported that cardiac and/or hypertensive patients under treatment with diuretics, ACE-inhibitors, and/or beta blocking agents are at higher risk of adverse reactions when administered iodinated contrast media.

Beta-blockers may impair the response to treatment of bronchospasm induced by contrast medium.

Patients with normal renal function can continue to take metformin normally. In diabetic patients with diabetic nephropathy, under treatment with metformin and with moderate renal impairment, metformin should be stopped at the time of, or prior to the procedure and withheld for 48 hours subsequent to the procedure and reinstituted only after renal function has been re-evaluated and found to be normal In emergency patients in whom renal function is either impaired or unknown, the physician shall weigh out risk and benefit of an examination with a contrast medium and take precautions. Metformin should be stopped from time of contrast medium administration. After the procedure the patient should be monitored for signs of lactic acidosis. Metformin should be restarted 48 hours after contrast medium if serum creatinine/eGFR is unchanged from the pre-imaging level.

Allergy-like reactions to contrast media are more frequent and may manifest as delayed reactions in patients treated with immuno-modulators, like Interleukin-2 (IL-2).

Epidural and intrathecal corticosteroids should never be concurrently administered when iodinated contrast media are used, because corticosteroids may promote and affect the signs and symptoms of arachnoiditis (see section 4.3 - Contraindications).

4.6 Fertility, pregnancy and lactation

Women of childbearing potential
Appropriate investigations and measures should be taken when exposing women of child-bearing potential to any X-ray examination, whether with or without contrast medium.

Pregnancy
Animal studies have not indicated any harmful effects with respect to the course of pregnancy or on the health of the unborn or neonate. The safety of iomeprol in human pregnancy however has not been established. Therefore avoid in pregnancy unless there is no safer alternative.
Since, wherever possible, exposure to radiation should be avoided during pregnancy, the benefits of any X ray examination, whether with or without contrast material, should for this reason alone be carefully weighed against the possible risk.

Breastfeeding
No human data exist concerning the excretion of iomeprol in breast milk. Animal studies have demonstrated that the excretion of iomeprol in breast milk is similar to that of other contrast agents and that these compounds are only minimally absorbed by the gastrointestinal tract of the young. Adverse effects on the nursing infant are therefore unlikely to occur.

Stopping breastfeeding is unnecessary.

4.7 Effects on ability to drive and use machines

There is no known effect on the ability to drive and operate machines.

After intrathecal administration, it is recommended that the patient should wait 24 hours before driving or operating machinery.

4.8 Undesirable effects

General

The use of iodinated contrast media may cause untoward side effects. They are usually mild to moderate and transient in nature. However, severe and life-threatening reactions sometimes leading to death have been reported. In most cases, reactions occur within minutes of dosing but at times reactions may occur at later time.

Anaphylaxis (anaphylactoid/hypersensitivity reactions) may manifest with various symptoms, and rarely does any one patient develop all the symptoms. Typically, in 1 to 15 min (but rarely after as long as 2 h), the patient complains of feeling abnormal, agitation, flushing, feeling hot, sweating increased, dizziness, increased lacrimation, rhinitis, palpitations, paresthesia, pruritus, sore throat and throat tightness, dysphagia, cough, sneezing, urticaria, erythema, mild localised oedema, angioneurotic oedema and dyspnoea due to glottic/laryngeal/pharyngeal oedema and/or spasm manifesting with wheezing, and bronchospasm.
Nausea, vomiting, abdominal pain, and diarrhoea are also reported.
These reactions, which can occur independently of the dose administered or the route of administration, may represent the first signs of circulatory collapse.
Administration of the contrast medium must be discontinued immediately and, if needed, appropriate specific treatment urgently initiated via venous access.
Severe reactions involving the cardiovascular system, such as vasodilatation, with pronounced hypotension, tachycardia, dyspnoea, agitation, cyanosis and loss of consciousness progressing to respiratory and/or cardiac arrest may result in death. These events can occur rapidly and require full and aggressive cardio-pulmonary resuscitation.
Primary circulatory collapse can occur as the only and/or initial presentation without respiratory symptoms or without other signs or symptoms outlined above.

The adverse reactions reported in clinical trials among 4,903 adult patients and from post-marketing surveillance are represented in the tables below by frequency and classified by MedDRA system organ class.

Within each frequency grouping, adverse reactions are presented in order of decreasing seriousness.

4.8.1 Intravascular administration

Adult patients involved in clinical trials with intravascular administration of Iomeprol were 4,515.

Adults
System Organ Class | Adverse Reactions
System Organ Class | Clinical Trials |  |  | Post-marketing Surveillance
System Organ Class | Common (≥1/100 t o <1/10) | Uncommon (≥1/1000 to <1/100) | Rare (≥1/10,000 to <1/1000) | Frequency unknown*
Blood and lymphatic system disorders |  |  |  | Thrombocytopenia, Haemolytic anaemia
Immune system disorders |  |  |  | Anaphylactoid reaction
Psychiatric disorders |  |  |  | Anxiety Confusional state
Nervous system disorders |  | Headache Dizziness | Presyncope | Coma Transient ischaemic attack Paralysis Syncope Convulsion Loss of consciousness Dysarthria Paraesthesia Amnesia Somnolence Taste abnormality
Eye disorders |  |  |  | Blindness transient Visual disturbance Conjunctivitis Lacrimation increased Photopsia
Cardiac disorders |  |  | Bradycardia Tachycardia Extrasystoles | Cardiac arrest Myocardial infarction Cardiac failure Angina pectoris Arrhythmia Ventricular or atrial fibrillation Atrioventricular block Palpitations Cyanosis
Vascular disorders |  | Hypertension | Hypotension | Circulatory collapse or shock Hot flush Flushing Pallor
Respiratory, thoracic and mediastinal disorders |  | Dyspnoea |  | Respiratory arrest Acute respiratory distress syndrome (ARDS) Pulmonary oedema Laryngeal oedema Pharyngeal oedema Bronchospasm Asthma Cough Hyperventilation Pharynx discomfort Laryngeal discomfort Rhinitis Dysphonia
Gastrointestinal disorders |  | Nausea Vomiting |  | Diarrhoea Abdominal pain Salivary hypersecretion Dysphagia Salivary gland enlargement
Skin and subcutaneous tissue disorders |  | Erythema Urticaria Pruritus | Rash | Acute generalized exanthematous pustulosis Angioedema Cold sweat Sweating increased
Musculoskeletal and connective tissue disorder |  |  | Back pain | Arthralgia
Renal and urinary disorders |  |  |  | Renal failure
General disorders and administration site conditions | Feeling hot | Chest pain Injection site warmth and pain | Asthenia Rigors Pyrexia | Injection site reaction** Coldness local Fatigue Malaise Thirst
Investigations |  |  | Blood creatinine increased | Electrocardiogram ST segment elevation Electrocardiogram abnormal
* Since the reactions were not observed during clinical trials with 4515 patients, best estimate is that their relative occurrence is rare (≥1/10,000 to <1/1000).
The most appropriate MedDRA term is used to describe a certain reaction and its symptoms and related conditions.
** Injection site reactions comprise injection site pain and swelling. In the majority of cases they are due to extravasation of contrast medium. These reactions are usually transient and result in recovery without sequelae. Cases of extravasation with inflammation, skin necrosis and even development of compartment syndrome have been reported.

Coronary artery thrombosis and coronary artery embolism have been reported as a complication of coronary catheterization procedures.

Vasospasm and consequent ischaemia have been observed during intra-arterial injections of contrast medium, in particular after coronary and cerebral angiography often procedurally related and possibly triggered by the tip of the catheter or excess catheter pressure.

As with other iodinated contrast media, very rare cases of mucocutaneous syndromes, including Stevens-Johnson syndrome, toxic epidermal necrolysis (Lyell syndrome) and erythema multiforme, have been reported following the administration of Iomeprol injection.

Paediatric patients

There is limited experience with paediatric patients. The clinical trial paediatric safety database comprises 167 patients.

The Iomeprol safety profile is similar in children and adults.

4.8.2 Intrathecal administration

Adults

Adults patients involved in clinical trials with intrathecal administration of Iomeprol were 388.

The most frequently reported adverse reactions following intrathecal administration of Iomeprol are headache, dizziness, nausea, vomiting and back pain. These reactions are usually mild to moderate and transient in nature. Rarely, headache may persist for days. Most side effects occur some hours (3 to 6 hours) after the procedure, due to the distribution of the contrast medium in the CSF circulation from the site of administration to the intravascular space (see section 5.2: Pharmacokinetic properties). Most reactions usually occur within 24 hours after injection.

System Organ Class | Adverse Reactions
System Organ Class | Clinical Trials |  |  | Post-marketing Surveillance
System Organ Class | Very common (≥1/10) | Common (≥1/100 to <1/10) | Uncommon (≥1/1000 to <1/100) | Frequency unknown*
Immune system disorders |  |  |  | Anaphylactoid reaction
Nervous system disorders | Headache | Dizziness | Hypoaesthesia Paraesthesia Paraparesis Loss of consciousness Somnolence | Epilepsy
Vascular disorders |  | Hypertension | Hypotension Flushing
Gastrointestinal disorders |  | Nausea Vomiting
Skin and subcutaneous tissue disorders |  |  | Hyperhidrosis Pruritus | Rash
Musculoskeletal and connective tissue disorder |  | Back pain Pain in extremity | Musculoskeletal stiffness Neck pain
General disorders and administration site conditions |  | Injection site reaction** | Feeling hot Pyrexia
* Since the reactions were not observed during clinical trials with 388 patients, best estimate is that their relative occurrence is uncommon (≥ 1/1000 to <1/100.
The most appropriate MedDRA term is used to describe a certain reaction and its symptoms and related conditions.
** Injection site reactions comprise application site pain, injection site discomfort, injection site pain and injection site warmth.

Paediatric patients

No adverse reactions were reported after intrathecal administration of Iomeprol both in clinical trials and in the post-marketing surveillance.

4.8.3 Administration to body cavities

After injection of an iodinated contrast media in body cavities, contrast media are slowly absorbed from the area of administration into the systemic circulation and subsequently cleared by renal elimination.

Blood amylase increased is common following ERCP. Very rare cases of pancreatitis have been described.

The reactions reported in cases of arthrography and fistulography usually represent irritative manifestations superimposed on pre-existing conditions of tissue inflammation.

Hypersensitivity reactions are rare, generally mild and in the form of skin reactions. However, the possibility of severe anaphylactoid reactions cannot be excluded.

As with other iodinated contrast media, pelvic pain and malaise may occur after hysterosalpingography.

Reporting of suspected adverse reactions
Reporting suspected adverse reactions after authorisation of the medicinal product is important. It allows continued monitoring of the benefit/risk balance of the medicinal product. Healthcare professionals are asked to report any suspected adverse reactions via the Yellow Card Scheme
Website: www.mhra.gov.uk/yellowcard or search for MHRA Yellow Card in the Google Play or Apple App Store.

4.9 Overdose

The effects of overdose on the pulmonary and cardiovascular systems may become life-threatening. Treatment consists of support of the vital functions and prompt use of symptomatic therapy. Iomeprol does not bind to plasma or serum proteins and is therefore dialyzable.

5 PHARMACOLOGICAL PROPERTIES

5.1 Pharmacodynamic properties

ATC code: V08AB10

Iomeprol is a low osmolality, non-ionic organic molecule with radio-opacity conferred by an iodine content of 49% of the molecular weight. It is formulated for use as an intravascular/intracavitary/ intrathecal contrast medium in concentrations of up to 400mg iodine per ml. Even at this concentration the low viscosity allows delivery of high doses through thin catheters.

5.2 Pharmacokinetic properties

The pharmacokinetics of intravascularly administered iomeprol are similar to those of other iodinated contrast media and conform to a two-compartment model with a rapid distribution and a slower elimination phase. In healthy subjects, the mean distribution and elimination half-lives of iomeprol were 0.5 hours and 1.9 hours respectively.

Distribution volume is similar to that of extra cellular fluid. There is no significant serum protein binding and iomeprol is not metabolized.

Elimination is almost exclusively through the kidneys (90% of the dose recovered in the urine within 96 hours of its administration) and is rapid (50% of an intravascularly administered dose within 2 hours).

Following intrathecal administration to animals, iomeprol is completely cleared from the CSF and passes into the plasma compartment.

5.3 Preclinical Safety Data

Pre-clinical data reveal no special hazard for humans based on conventional studies of safety pharmacology, repeated dose toxicity, genotoxicity, toxicity to reproduction.

Results from studies in rats, mice and dogs demonstrate that iomeprol has an acute intravenous or intra-arterial toxicity similar to that of the other non ionic contrast media, as well as a good systemic tolerability after repeated intravenous administrations in rats and dogs.

6. PHARMACEUTICAL PARTICULARS

6.1 List of excipients

trometamol
hydrochloric acid
water for injection

6.2 Incompatibilities

In the absence of compatibility studies, this medicinal product must not be mixed with other medicinal products.

6.3 Shelf Life

Five years

6.4 Special precautions for storage

Store below 30°C
Protect from light

6.5 Nature and contents of container

Colourless Type I or Type II glass bottles with rubber/aluminium cap.
Quantities of 20, 30, 50, 75, 100, 150, 200 or 250 ml of solution.

6.6 Special precautions for disposal and other handling

Bottles containing contrast media solution are not intended for the withdrawal of multiple doses. The rubber stopper should never be pierced more than once. The use of proper withdrawal cannulas for piercing the stopper and drawing up the contrast medium is recommended.

Before use, examine the product to assure that the container and closure have not been damaged. Do not use the solution if it is discolored or particulate matter is present.

The contrast medium should not be drawn into the syringe until immediately before use. Withdrawal of contrast agents from their containers should be accomplished under aseptic conditions with sterile syringes. Sterile techniques must be used with any spinal puncture or intravascular injection, and with catheters and guidewires. If non-disposable equipment is used, scrupulous care should be taken to prevent residual contamination with traces of cleansing agents.

It is desirable that solutions of contrast media for intravascular and intrathecal use should be at body temperature when injected.

Any residue of contrast medium in the syringe must be discarded. Solutions not used in one examination session or waste material, such as the connecting tubes, should be disposed in accordance with local requirements.

7. MARKETING AUTHORISATION HOLDER

Bracco UK Ltd
Magdalen Centre
The Oxford Science Park
Oxford, OX4 4GA
United Kingdom

8. MARKETING AUTHORISATION NUMBER

18920/0004

9. DATE OF FIRST AUTHORISATION/RENEWAL OF AUTHORISATION

11 December 1992 / 29 December 1998

10. DATE OF REVISION OF THE TEXT

19 January 2022

MEDICATION GUIDE

1. NAME OF THE MEDICINAL PRODUCT

Iomeron 350, solution for injection

2. QUALITATIVE AND QUANTITATIVE COMPOSITION

Contains 71.44% w/v of iomeprol equivalent to 35% iodine or 350mg iodine/ml.

For the full list of excipients, see section 6.1.For excipients, see 6.1.

3. PHARMACEUTICAL FORM

Solution for injection.

4. CLINICAL PARTICULARS

4.1 Therapeutic indications

X-ray contrast medium used for:

- peripheral arteriography
- venography
- aortography
- angiocardiography and left ventriculography
- coronary arteriography
- visceral arteriography
- digital subtraction angiography
- computed tomography enhancement
- urography
- dacryocystography
- sialography
- fistulography
- galactography

4.2 Posology and method of administration

peripheral arteriography |  | adults | 10 - 90ml *
 |  | children | * *
venography |  | adults | 10 - 100ml* max 250ml 10 - 50ml upper extremity 50 - 100 lower extremity
aortography |  | adults | 50 - 80ml
 |  | children | * *
angiocardiography and left ventriculography |  | adults | 30 - 80ml max 250ml
 |  | children | * *
coronary arteriography |  | adults | 4 - 10ml per artery *
visceral arteriography |  | adults | 5 - 50ml* or according to type of examination; max 250ml
 |  | children | * *
digital subtraction angiography
 | intravenous | adults | 30 - 60ml* max 250ml
computed tomography
 | brain | adults | 50 - 150ml
 |  | children | * *
 | body | adults | 40 - 150ml max 250ml
 |  | children | * *
Urography
 | intravenous | adults | 50 - 150ml
 |  | neonates | 3 - 4.8ml/kg
 |  | babies | 2.5 - 4ml
 |  | children | 1 - 2.5ml/kg or *
 | arthrography | adults | up to 10ml
 | dacryocystography | adults | 3 - 8ml
 | sialography | adults | 1 - 3ml
 | fistulography | adults | 1 - 50ml
 | galactography | adults | 0.2 - 1.5ml
* Repeat as necessary
* * According to body size and age

In elderly patients the lowest effective dose should be used.
Unless otherwise instructed by the doctor, a normal diet may be maintained on the day of the examination.

The X ray can be taken up to 60 minutes following injection.

4.3 Contraindications

Hypersensitivity to the active substance or any of the excipients.

4.4 Special warnings and special precautions for use

In consideration of possible complications, the patient should be kept under observation for at least 30 minutes after the examination.

Extreme caution during injection of contrast media is necessary to avoid extravasation.

Hydration
Patients must be well hydrated, and any relevant abnormalities of fluid or electrolyte balance should be corrected prior to and following contrast media injection. Especially patients with diabetes mellitus, polyuria, oligouria, hyperuricaemia, infants, small children, and elderly patients, should not be exposed to dehydration. Also patients with severely compromised hepatic and renal impairment are more at risk. Caution should be exercised in hydrating patients with underlying conditions that may be worsened by fluid overload, including congestive heart failure.

Rehydration prior to use of iomeprol is recommended in patients with sickle cell disease.

Special population
Hypersensitivity to iodinated contrast media, allergic predisposition
A positive history of allergy, asthma or untoward reaction during previous similar investigations indicates a need for extra caution since, as with other contrast media, this product may provoke anaphylaxis or other manifestations of allergy with nausea, vomiting, dyspnoea, erythema, urticaria and hypotension. The benefits should clearly outweigh the risks in such patients and appropriate resuscitative measures should be immediately available. The primary treatments are as follows:

Effect | Major Symptoms | Primary Treatment
Vasomotor effect | warmth nausea/vomiting | reassurance
Cutaneous | scattered hives severe urticaria | H1-antihistamines H2-antihistamines
Bronchospastic | wheezing | oxygen Beta-2-agonist inhalers
Anaphylactoid | angioedema | oxygen
reaction | urticaria bronchospasm hypotension | iv fluids adrenergics (iv epinephrine) Inhaled beta-2-adrenergics
 |  | antihistamines (H1-and H2- blockers) corticosteroids
Hypotensive | hypotension | iv fluids
Vagal reaction | hypotension bradycardia | iv fluids iv atropine

From: Bush WH; The Contrast Media Manual; Katzburg RW Ed.; Williams and Wilkins; Baltimore 1992; Chapter 2 p 23

The risk of bronchospasm-inducing reactions in asthmatic patients is higher after contrast media administration, especially in patients taking beta-blockers.

Hypersensitivity testing
In patients with suspected or known hypersensitivity to contrast media, sensitivity test doses are not recommended, as severe or fatal reactions to contrast media are not predictable from sensitivity test.

Myelomatosis or paraproteinaemias are conditions predisposing to renal impairment following CM administration. The benefits of the use of a contrast-enhanced procedure should be carefully weighted against the possible risk. Adequate hydration and monitoring of renal function are recommended after CM administration.

Cardiovascular diseases
Care should be taken in severe cardiac disease particularly heart failure and coronary artery disease. Reactions may include pulmonary oedema, haemodynamic changes, ischaemic ECG changes and arrhythmias.
In severe, chronic hypertension the risk of renal damage following administration of a contrast medium is increased. In these cases the risks associated with the catheterization procedure are increased.

The product should be used with caution in patients with hyperthyroidism or goitre. Use may interfere with thyroid function tests.

The administration of iodinated contrast media may aggravate myasthenia signs and symptoms.

CNS Disorders
Particular care is needed in patients with acute cerebral infarction, acute intracranial haemorrhage and any conditions involving damage to the blood brain barrier, brain oedema or acute demyelination. Convulsive seizures are more likely in patients with intracranial tumours or metastases or with a history of epilepsy.

Neurological symptoms related to cerebrovascular diseases, intracranial tumours/metastases or degenerative or inflammatory pathologies may be exacerbated.

There is an increased risk of transient neurological complications in patients with symptomatic cerebrovascular disease eg stroke, transient ischaemic attacks. Cerebral ischaemic phenomena may be caused by intravascular injection.

Anticonvulsant therapy should not be discontinued.

In acute and chronic alcoholism the increase in blood brain barrier permeability facilitates the passage of contrast medium into cerebral tissue possibly leading to CNS disorders. There is a possibility of a reduced seizure threshold in alcoholics.

In patients with a drug addiction there is also the possibility of a reduced seizure threshold.

Patients with phaeochromocytoma may develop severe, occasionally uncontrollable hypertensive crises during intra-arterial administration. Premedication with an alpha and beta receptor blocker is recommended in these patients. Pronounced excitement, anxiety and pain can cause side effects or intensify reaction to the contrast medium. A sedative may be given.

Renal impairment
In patients with moderate to severe impairment of renal function, attention should be paid to renal function parameters before re-examining the patient with a contrast media.
Preventive measures include:

- identification of high-risk patients;
- ensuring adequate hydration before CM administration, preferably by maintaining i.v. infusion before and during the procedure and until the CM has been cleared by the kidneys;

avoiding whenever possible, the administration of nephrotoxic drugs or major surgery or procedure such as renal angioplasty, until the CM has been cleared;

A combination of severe hepatic and renal impairment delays excretion of the contrast medium therefore such patients should not be examined unless absolutely necessary.

Diabetes mellitus
Care should be taken in renal impairment and diabetes. In these patients it is important to maintain hydration in order to minimise deterioration in renal function.
The presence of renal damage in diabetic patients is one of the factors predisposing to renal impairment following contrast media administration. This may precipitate lactic acidosis in patients who are taking metformin (see section 4.5 - Interaction with medicaments and other forms of interaction).

Children: Infants up to 1 year, especially the new-born, are particularly susceptible to electrolyte imbalance and haemodynamic alterations. Care should be taken regarding the dosage used.

Transient hypothyroidism may occur in neonates when the mother or the neonate has received an iodinated contrast agent. Thyroid function tests (usually TSH and T4) are recommended in neonates 7-10 days and 1 month after exposure to Iomeron especially in preterm neonates.

Elderly: There is special risk of reactions involving the circulatory system such that myocardial ischaemia, major arrhythmias and extrasystoles are more likely to occur. A combination of neurological disturbances and vascular pathologies present a serious complication. The probability of acute renal insufficiencies is higher in these people.

Precautions for dedicated exams
Angiography
Non ionic contrast media have less antiocoagulant activity in vitro than ionic media. Meticulous attention should therefore be paid to angiographic technique. Non ionic media should not be allowed to remain in contact with blood in a syringe, and intravascular catheters should be flushed frequently to minimise the risk of clotting which, rarely, has led to serious thromboembolic complications.

Intravascular administration should be performed if possible with the patient lying down. The patient should be kept in this position and closely observed for at least 30 minutes after the procedure since the majority of severe incidents occur with this time.

Venography
Special care is required when venography is performed in patients with thrombosis, phlebitis, severe ischaemic disease, local infection or a totally obstructed artero-venous system.

4.5 Interaction with other medicaments and other forms of interaction

Use of the product may interfere with tests for thyroid function. Vasopressor agents should not be administered prior to iomeprol.

Treatment with drugs that lower the seizure threshold such as certain neuroleptics (MAO inhibitors, tricyclic antidepressants), analeptics, and anti-emetics and phenotiazine derivatives should be discontinued 48 hours before the examination. Treatment should not be resumed until 24 hours post-procedure.

It has been reported that cardiac and/or hypertensive patients under treatment with diuretics, ACE-inhibitors, and/or beta blocking agents are at higher risk of adverse reactions when administered iodinated contrast media.

Beta-blockers may impair the response to treatment of bronchospasm induced by contrast medium.

Patients with normal renal function can continue to take metformin normally. In diabetic patients with diabetic nephropathy, under treatment with metformin and with moderate renal impairment, metformin should be stopped at the time of, or prior to the procedure and withheld for 48 hours subsequent to the procedure and reinstituted only after renal function has been re-evaluated and found to be normal In emergency patients in whom renal function is either impaired or unknown, the physician shall weigh out risk and benefit of an examination with a contrast medium and take precautions. Metformin should be stopped from time of contrast medium administration. After the procedure the patient should be monitored for signs of lactic acidosis. Metformin should be restarted 48 hours after contrast medium if serum creatinine/eGFR is unchanged from the pre-imaging level.

Allergy-like reactions to contrast media are more frequent and may manifest as delayed reactions in patients treated with immuno-modulators, like Interleukin-2 (IL-2).

4.6 Fertility, pregnancy and lactation

Women of childbearing potential
Appropriate investigations and measures should be taken when exposing women of child-bearing potential to any X-ray examination, whether with or without contrast medium.

Pregnancy
Animal studies have not indicated any harmful effects with respect to the course of pregnancy or on the health of the unborn or neonate. The safety of iomeprol in human pregnancy however has not been established. Therefore avoid in pregnancy unless there is no safer alternative.

Breastfeeding
No human data exist concerning the excretion of iomeprol in breast milk. Animal studies have demonstrated that the excretion of iomeprol in breast milk is similar to that of other contrast agents and that these compounds are only minimally absorbed by the gastrointestinal tract of the young. Adverse effects on the nursing infant are therefore unlikely to occur.
Stopping breastfeeding is unnecessary.

4.7 Effects on ability to drive and use machines

There is no known effect on the ability to drive and operate machines.

4.8 Undesirable effects

General

The use of iodinated contrast media may cause untoward side effects. They are usually mild to moderate and transient in nature. However, severe and life-threatening reactions sometimes leading to death have been reported. In most cases, reactions occur within minutes of dosing but at times reactions may occur at later time.

Anaphylaxis (anaphylactoid/hypersensitivity reactions) may manifest with various symptoms, and rarely does any one patient develop all the symptoms. Typically, in 1 to 15 min (but rarely after as long as 2 h), the patient complains of feeling abnormal, agitation, flushing, feeling hot, sweating increased, dizziness, increased lacrimation, rhinitis, palpitations, paresthesia, pruritus, sore throat and throat tightness, dysphagia, cough, sneezing, urticaria, erythema, mild localised oedema, angioneurotic oedema and dyspnoea due to glottic/laryngeal/pharyngeal oedema and/or spasm manifesting with wheezing, and bronchospasm.
Nausea, vomiting, abdominal pain, and diarrhoea are also reported.
These reactions, which can occur independently of the dose administered or the route of administration, may represent the first signs of circulatory collapse.
Administration of the contrast medium must be discontinued immediately and, if needed, appropriate specific treatment urgently initiated via venous access.
Severe reactions involving the cardiovascular system, such as vasodilatation, with pronounced hypotension, tachycardia, dyspnoea, agitation, cyanosis and loss of consciousness progressing to respiratory and/or cardiac arrest may result in death. These events can occur rapidly and require full and aggressive cardio-pulmonary resuscitation.
Primary circulatory collapse can occur as the only and/or initial presentation without respiratory symptoms or without other signs or symptoms outlined above.

The adverse reactions reported in clinical trials among 4,903 adult patients and from post-marketing surveillance are represented in the tables below by frequency and classified by MedDRA system organ class.

Within each frequency grouping, adverse reactions are presented in order of decreasing seriousness.

4.8.1 Intravascular administration

Adult patients involved in clinical trials with intravascular administration of Iomeprol were 4,515.

Adults
System Organ Class | Adverse Reactions
System Organ Class | Clinical Trials |  |  | Post-marketing Surveillance
System Organ Class | Common (≥1/100 t o <1/10) | Uncommon (≥1/1000 to <1/100) | Rare (≥1/10,000 to <1/1000) | Frequency unknown*
Blood and lymphatic system disorders |  |  |  | Thrombocytopenia, Haemolytic anaemia
Immune system disorders |  |  |  | Anaphylactoid reaction
Psychiatric disorders |  |  |  | Anxiety Confusional state
Nervous system disorders |  | Headache Dizziness | Presyncope | Coma Transient ischaemic attack Paralysis Syncope Convulsion Loss of consciousness Dysarthria Paraesthesia Amnesia Somnolence Taste abnormality
Eye disorders |  |  |  | Blindness transient Visual disturbance Conjunctivitis Lacrimation increased Photopsia
Cardiac disorders |  |  | Bradycardia Tachycardia Extrasystoles | Cardiac arrest Myocardial infarction Cardiac failure Angina pectoris Arrhythmia Ventricular or atrial fibrillation Atrioventricular block Palpitations Cyanosis
Vascular disorders |  | Hypertension | Hypotension | Circulatory collapse or shock Hot flush Flushing Pallor
Respiratory, thoracic and mediastinal disorders |  | Dyspnoea |  | Respiratory arrest Acute respiratory distress syndrome (ARDS) Pulmonary oedema Laryngeal oedema Pharyngeal oedema Bronchospasm Asthma Cough Hyperventilation Pharynx discomfort Laryngeal discomfort Rhinitis Dysphonia
Gastrointestinal disorders |  | Nausea Vomiting |  | Diarrhoea Abdominal pain Salivary hypersecretion Dysphagia Salivary gland enlargement
Skin and subcutaneous tissue disorders |  | Erythema Urticaria Pruritus | Rash | Acute generalized exanthematous pustulosis Angioedema Cold sweat Sweating increased
Musculoskeletal and connective tissue disorder |  |  | Back pain | Arthralgia
Renal and urinary disorders |  |  |  | Renal failure
General disorders and administration site conditions | Feeling hot | Chest pain Injection site warmth and pain | Asthenia Rigors Pyrexia | Injection site reaction** Coldness local Fatigue Malaise Thirst
Investigations |  |  | Blood creatinine increased | Electrocardiogram ST segment elevation Electrocardiogram abnormal
* Since the reactions were not observed during clinical trials with 4515 patients, best estimate is that their relative occurrence is rare (≥1/10,000 to <1/1000).
The most appropriate MedDRA term is used to describe a certain reaction and its symptoms and related conditions.
** Injection site reactions comprise injection site pain and swelling. In the majority of cases they are due to extravasation of contrast medium. These reactions are usually transient and result in recovery without sequelae. Cases of extravasation with inflammation, skin necrosis and even development of compartment syndrome have been reported.

Coronary artery thrombosis and coronary artery embolism have been reported as a complication of coronary catheterization procedures.

Vasospasm and consequent ischaemia have been observed during intra-arterial injections of contrast medium, in particular after coronary and cerebral angiography often procedurally related and possibly triggered by the tip of the catheter or excess catheter pressure.

As with other iodinated contrast media, very rare cases of mucocutaneous syndromes, including Stevens-Johnson syndrome, toxic epidermal necrolysis (Lyell syndrome) and erythema multiforme, have been reported following the administration of Iomeprol injection.

Paediatric patients

There is limited experience with paediatric patients. The clinical trial paediatric safety database comprises 167 patients.

The Iomeprol safety profile is similar in children and adults.

4.8.2 Administration to body cavities

After injection of an iodinated contrast media in body cavities, contrast media are slowly absorbed from the area of administration into the systemic circulation and subsequently cleared by renal elimination.

Blood amylase increased is common following ERCP. Very rare cases of pancreatitis have been described.

The reactions reported in cases of arthrography and fistulography usually represent irritative manifestations superimposed on pre-existing conditions of tissue inflammation.

Hypersensitivity reactions are rare, generally mild and in the form of skin reactions. However, the possibility of severe anaphylactoid reactions cannot be excluded.
As with other iodinated contrast media, pelvic pain and malaise may occur after hysterosalpingography.

Reporting of suspected adverse reactions
Reporting suspected adverse reactions after authorisation of the medicinal product is important. It allows continued monitoring of the benefit/risk balance of the medicinal product. Healthcare professionals are asked to report any suspected adverse reactions via the Yellow Card Scheme
Website: www.mhra.gov.uk/yellowcard or search for MHRA Yellow Card in the Google Play or Apple App Store.

4.9 Overdose

The effects of overdose on the pulmonary and cardiovascular systems may become life-threatening. Treatment consists of support of the vital functions and prompt use of symptomatic therapy. Iomeprol does not bind to plasma or serum proteins and is therefore dialyzable.

5 PHARMACOLOGICAL PROPERTIES

5.1 Pharmacodynamic properties

ATC code: V08AB10

Iomeprol is a low osmolality, non-ionic organic molecule with radio-opacity conferred by an iodine content of 49% of the molecular weight. It is formulated for use as an intravascular/intracavitary contrast medium in concentrations of up to 400mg iodine per ml. Even at this concentration the low viscosity allows delivery of high doses through thin catheters.

5.2 Pharmacokinetic properties

The pharmacokinetics of intravascularly administered iomeprol are similar to those of other iodinated contrast media and conform to a two-compartment model with a rapid distribution and a slower elimination phase. In healthy subjects, the mean distribution and elimination half-lives of iomeprol were 0.5 hours and 1.9 hours respectively.

Distribution volume is similar to that of extra cellular fluid. There is no significant serum protein binding and iomeprol is not metabolized.

Elimination is almost exclusively through the kidneys (90% of the dose recovered in the urine within 96 hours of its administration) and is rapid (50% of an intravascularly administered dose within 2 hours).

5.3 Preclinical Safety Data

Pre-clinical data reveal no special hazard for humans based on conventional studies of safety pharmacology, repeated dose toxicity, genotoxicity, toxicity to reproduction.

Results from studies in rats, mice and dogs demonstrate that iomeprol has an acute intravenous or intra-arterial toxicity similar to that of the other non ionic contrast media, as well as a good systemic tolerability after repeated intravenous administrations in rats and dogs.

6. PHARMACEUTICAL PARTICULARS

6.1 List of excipients

trometamol
hydrochloric acid
water for injection

6.2 Incompatibilities

In the absence of compatibility studies, this medicinal product must not be mixed with other medicinal products. No other drug should be mixed with the contrast medium.

6.3 Shelf Life

Five years

6.4 Special precautions for storage

Store below 30°C
Protect from light

6.5 Nature and contents of containers

Colourless Type I or Type II glass bottles with rubber/aluminium cap.
Quantities of 20, 30, 50, 75, 100, 150, 200 or 250 ml of solution.

6.6 Special precautions for disposal and other handling

Bottles containing contrast media solution are not intended for the withdrawal of multiple doses. The rubber stopper should never be pierced more than once. The use of proper withdrawal cannulas for piercing the stopper and drawing up the contrast medium is recommended.

Before use, examine the product to assure that the container and closure have not been damaged. Do not use the solution if it is discolored or particulate matter is present.

The contrast medium should not be drawn into the syringe until immediately before use. Withdrawal of contrast agents from their containers should be accomplished under aseptic conditions with sterile syringes. Sterile techniques must be used with any spinal puncture or intravascular injection, and with catheters and guidewires. If non-disposable equipment is used, scrupulous care should be taken to prevent residual contamination with traces of cleansing agents.

It is desirable that solutions of contrast media for intravascular and intrathecal use should be at body temperature when injected.

Any residue of contrast medium in the syringe must be discarded. Solutions not used in one examination session or waste material, such as the connecting tubes, should be disposed in accordance with local requirements.

7. MARKETING AUTHORISATION HOLDER

Bracco UK Ltd
Magdalen Centre
The Oxford Science Park
Oxford, OX4 4GA
United Kingdom

8. MARKETING AUTHORISATION NUMBER

18920/0005

9. DATE OF FIRST AUTHORISATION/RENEWAL OF AUTHORISATION

11 December 1992 / 29 December 1998

10. DATE OFREVISION OF THE TEXT

19 January 2022

MEDICATION GUIDE

1. NAME OF THE MEDICINAL PRODUCT

Iomeron 400, solution for injection

2. QUALITATIVE AND QUANTITATIVE COMPOSITION

Contains 81.65% w/v of iomeprol equivalent to 40% iodine or 400mg iodine/ml.

For the full list of excipients, see section 6.1.For excipients, see 6.1.

3. PHARMACEUTICAL FORM

Solution for injection.

4. CLINICAL PARTICULARS

4.1 Therapeutic indications

X-ray contrast medium used for:

- peripheral arteriography
- aortography
- angiocardiography and left ventriculography
- coronary arteriography
- visceral arteriography
- digital subtraction angiography
- computed tomography enhancement
- urography
- dacryocystography
- sialography
- fistulography
- galactography

4.2 Posology and method of administration

peripheral arteriography |  | adults | 10 - 90ml *
 |  | children | * *
aortography |  | adults | 50 - 80ml
 |  | children | * *
angiocardiography and left ventriculography |  | adults | 30 - 80ml max 250ml
 |  | children | * *
coronary arteriography |  | adults | 4 - 10ml per artery *
visceral arteriography |  | adults | 5 - 50ml* or according to type of examination;
 |  | children | * *
digital subtraction angiography
intravenous |  | adults | 30 - 60ml* max 250ml
computed tomography
body |  | adults | 40 - 150ml max 250ml
 |  | children | * *
urography
intravenous |  | adults | 50 - 150ml
 |  | neonates | 3 - 4.8ml/kg
 |  | babies | 2.5 - 4ml
 |  | children | 1 - 2.5ml/kg or *
dacryocystography |  | adults | 3 - 8ml
sialography |  | adults | 1 - 3ml
fistulography |  | adults | 1 - 50ml
galactography |  | adults | 0.2 - 1.5ml
* Repeat as necessary
* * According to body size and age

In elderly patients the lowest effective dose should be used.
Unless otherwise instructed by the doctor, a normal diet may be maintained on the day of the examination.

The X ray can be taken up to 60 minutes following injection.

4.3 Contraindications

Hypersensitivity to the active substance or any of the excipients.

4.4 Special warnings and special precautions for use

In consideration of possible complications, the patient should be kept under observation for at least 30 minutes after the examination.

Extreme caution during injection of contrast media is necessary to avoid extravasation.

Hydration
Patients must be well hydrated, and any relevant abnormalities of fluid or electrolyte balance should be corrected prior to and following contrast media injection. Especially patients with diabetes mellitus, polyuria, oligouria, hyperuricaemia, infants, small children, and elderly patients, should not be exposed to dehydration. Also patients with severely compromised hepatic and renal impairment are more at risk. Caution should be exercised in hydrating patients with underlying conditions that may be worsened by fluid overload, including congestive heart failure.

Rehydration prior to use of iomeprol is recommended in patients with sickle cell disease.

Special population
Hypersensitivity to iodinated contrast media, allergic predisposition
A positive history of allergy, asthma or untoward reaction during previous similar investigations indicates a need for extra caution since, as with other contrast media, this product may provoke anaphylaxis or other manifestations of allergy with nausea, vomiting, dyspnoea, erythema, urticaria and hypotension. The benefits should clearly outweigh the risks in such patients and appropriate resuscitative measures should be immediately available. The primary treatments are as follows:

Effect | Major Symptoms | Primary Treatmen
Vasomotor effect | warmth nausea/vomiting | reassurance
Cutaneous | scattered hives severe urticaria | H1-antihistamines H2-antihistamines
Bronchospastic | wheezing | oxygen Beta-2-agonist inhalers
Anaphylactoid | angioedema | oxygen
reaction | urticaria bronchospasm hypotension | iv fluids adrenergics (iv epinephrine) Inhaled beta-2-adrenergics
 |  | antihistamines (H1-and H2- blockers) corticosteroids
Hypotensive | hypotension | iv fluids
Vagal reaction | hypotension bradycardia | iv fluids iv atropine

From: Bush WH; The Contrast Media Manual; Katzburg RW Ed.; Williams and Wilkins; Baltimore 1992; Chapter 2 p 23

The risk of bronchospasm-inducing reactions in asthmatic patients is higher after contrast media administration, especially in patients taking beta-blockers.

Hypersensitivity testing
In patients with suspected or known hypersensitivity to contrast media, sensitivity test doses are not recommended, as severe or fatal reactions to contrast media are not predictable from sensitivity test.

Myelomatosis or paraproteinaemias are conditions predisposing to renal impairment following CM administration. The benefits of the use of a contrast-enhanced procedure should be carefully weighted against the possible risk. Adequate hydration and monitoring of renal function are recommended after CM administration.

Cardiovascular diseases
Care should be taken in severe cardiac disease particularly heart failure and coronary artery disease. Reactions may include pulmonary oedema, haemodynamic changes, ischaemic ECG changes and arrhythmias.
In severe, chronic hypertension the risk of renal damage following administration of a contrast medium is increased. In these cases the risks associated with the catheterization procedure are increased.

The product should be used with caution in patients with hyperthyroidism or goitre. Use may interfere with thyroid function tests.

The administration of iodinated contrast media may aggravate myasthenia signs and symptoms.

CNS Disorders
Particular care is needed in patients with acute cerebral infarction, acute intracranial haemorrhage and any conditions involving damage to the blood brain barrier, brain oedema or acute demyelination. Convulsive seizures are more likely in patients with intracranial tumours or metastases or with a history of epilepsy.

Neurological symptoms related to cerebrovascular diseases, intracranial tumours/metastases or degenerative or inflammatory pathologies may be exacerbated.

There is an increased risk of transient neurological complications in patients with symptomatic cerebrovascular disease eg stroke, transient ischaemic attacks. Cerebral ischaemic phenomena may be caused by intravascular injection.

Anticonvulsant therapy should not be discontinued.

In acute and chronic alcoholism the increase in blood brain barrier permeability facilitates the passage of the contrast medium into cerebral tissue possibly leading to CMS disorders. There is a possibility of a reduced seizure threshold in alcoholics.

In patients with a drug addiction there is also the possibility of a reduced seizure threshold.

Patients with phaeochromocytoma may develop severe, occasionally uncontrollable hypertensive crises during intra-arterial administration. Premedication with an alpha and beta receptor blocker is recommended in these patients. Pronounced excitement, anxiety and pain can cause side effects or intensify reaction to the contrast medium. A sedative may be given.

Renal impairment
In patients with moderate to severe impairment of renal function, attention should be paid to renal function parameters before re-examining the patient with a contrast media.
Preventive measures include:

- identification of high-risk patients;
- ensuring adequate hydration before CM administration, preferably by maintaining i.v. infusion before and during the procedure and until the CM has been cleared by the kidneys;

avoiding whenever possible, the administration of nephrotoxic drugs or major surgery or procedure such as renal angioplasty, until the CM has been cleared;
A combination of severe hepatic and renal impairment delays excretion of the contrast medium therefore such patients should not be examined unless absolutely necessary.

Diabetes mellitus
Care should be taken in renal impairment and diabetes. In these patients it is important to maintain hydration in order to minimise deterioration in renal function.
The presence of renal damage in diabetic patients is one of the factors predisposing to renal impairment following contrast media administration. This may precipitate lactic acidosis in patients who are taking metformin (see section 4.5 - Interaction with medicaments and other forms of interaction).

Children: Infants up to 1 year, especially the newborn, are particularly susceptible to electrolyte imbalance and haemodynamic alterations. Care should be taken regarding the dosage used.

Transient hypothyroidism may occur in neonates when the mother or the neonate has received an iodinated contrast agent. Thyroid function tests (usually TSH and T4) are recommended in neonates 7-10 days and 1 month after exposure to Iomeron especially in preterm neonates.

Elderly: There is special risk of reactions involving the circulatory system such that myocardial ischaemia, major arrhythmias and extrasystoles are more likely to occur. A combination of neurological disturbances and vascular pathologies present a serious complication. The probability of acute renal insufficiencies is higher in these people.

Precautions for dedicated exams

Angiography
Non ionic contrast media have less antiocoagulant activity in vitro than ionic media. Meticulous attention should therefore be paid to angiographic technique. Non ionic media should not be allowed to remain in contact with blood in a syringe, and intravascular catheters should be flushed frequently to minimise the risk of clotting which, rarely, has led to serious thromboembolic complications.

Intravascular administration should be performed if possible with the patient lying down. The patient should be kept in this position and closely observed for at least 30 minutes after the procedure since the majority of severe incidents occur with this time.

Venography
Special care is required when venography is performed in patients with thrombosis, phlebitis, severe ischaemic disease, local infection or a totally obstructed artero-venous system.

4.5 Interaction with other medicaments and other forms of interaction

Use of the product may interfere with tests for thyroid function. Vasopressor agents should not be administered prior to iomeprol.

Treatment with drugs that lower the seizure threshold such as certain neuroleptics (MAO inhibitors, tricyclic antidepressants), analeptics, and anti-emetics and phenotiazine derivatives should be discontinued 48 hours before the examination. Treatment should not be resumed until 24 hours post-procedure.

It has been reported that cardiac and/or hypertensive patients under treatment with diuretics, ACE-inhibitors, and/or beta blocking agents are at higher risk of adverse reactions when administered iodinated contrast media.

Beta-blockers may impair the response to treatment of bronchospasm induced by contrast medium.

Patients with normal renal function can continue to take metformin normally. In diabetic patients with diabetic nephropathy, under treatment with metformin and with moderate renal impairment, metformin should be stopped at the time of, or prior to the procedure and withheld for 48 hours subsequent to the procedure and reinstituted only after renal function has been re-evaluated and found to be normal In emergency patients in whom renal function is either impaired or unknown, the physician shall weigh out risk and benefit of an examination with a contrast medium and take precautions. Metformin should be stopped from time of contrast medium administration. After the procedure the patient should be monitored for signs of lactic acidosis. Metformin should be restarted 48 hours after contrast medium if serum creatinine/eGFR is unchanged from the pre-imaging level.

Allergy-like reactions to contrast media are more frequent and may manifest as delayed reactions in patients treated with immuno-modulators, like Interleukin-2 (IL-2).

4.6 Fertility, pregnancy and lactation

Women of childbearing potential
Appropriate investigations and measures should be taken when exposing women of child-bearing potential to any X-ray examination, whether with or without contrast medium.

Pregnancy
Animal studies have not indicated any harmful effects with respect to the course of pregnancy or on the health of the unborn or neonate. The safety of iomeprol in human pregnancy however has not been established. Therefore avoid in pregnancy unless there is no safer alternative.
Since, wherever possible, exposure to radiation should be avoided during pregnancy, the benefits of any X ray examination, whether with or without contrast material, should for this reason alone be carefully weighed against the possible risk

Breastfeeding
No human data exist concerning the excretion of iomeprol in breast milk. Animal studies have demonstrated that the excretion of iomeprol in breast milk is similar to that of other contrast agents and that these compounds are only minimally absorbed by the gastrointestinal tract of the young. Adverse effects on the nursing infant are therefore unlikely to occur.

Stopping breastfeeding is unnecessary.

4.7 Effects on ability to drive and use machines

There is no known effect on the ability to drive and operate machines.

4.8 Undesirable effects

General

The use of iodinated contrast media may cause untoward side effects. They are usually mild to moderate and transient in nature. However, severe and life-threatening reactions sometimes leading to death have been reported. In most cases, reactions occur within minutes of dosing but at times reactions may occur at later time.

Anaphylaxis (anaphylactoid/hypersensitivity reactions) may manifest with various symptoms, and rarely does any one patient develop all the symptoms. Typically, in 1 to 15 min (but rarely after as long as 2 h), the patient complains of feeling abnormal, agitation, flushing, feeling hot, sweating increased, dizziness, increased lacrimation, rhinitis, palpitations, paresthesia, pruritus, sore throat and throat tightness, dysphagia, cough, sneezing, urticaria, erythema, mild localised oedema, angioneurotic oedema and dyspnoea due to glottic/laryngeal/pharyngeal oedema and/or spasm manifesting with wheezing, and bronchospasm.
Nausea, vomiting, abdominal pain, and diarrhoea are also reported.
These reactions, which can occur independently of the dose administered or the route of administration, may represent the first signs of circulatory collapse.
Administration of the contrast medium must be discontinued immediately and, if needed, appropriate specific treatment urgently initiated via venous access.
Severe reactions involving the cardiovascular system, such as vasodilatation, with pronounced hypotension, tachycardia, dyspnoea, agitation, cyanosis and loss of consciousness progressing to respiratory and/or cardiac arrest may result in death. These events can occur rapidly and require full and aggressive cardio-pulmonary resuscitation.
Primary circulatory collapse can occur as the only and/or initial presentation without respiratory symptoms or without other signs or symptoms outlined above.

The adverse reactions reported in clinical trials among 4,903 adult patients and from post-marketing surveillance are represented in the tables below by frequency and classified by MedDRA system organ class.
Within each frequency grouping, adverse reactions are presented in order of decreasing seriousness.

4.8.1 Intravascular administration

Adult patients involved in clinical trials with intravascular administration of Iomeprol were 4,515.

Adults
System Organ Class | Adverse Reactions
System Organ Class | Clinical Trials |  |  | Post-marketing Surveillance
System Organ Class | Common (≥1/100 t o <1/10) | Uncommon (≥1/1000 to <1/100) | Rare (≥1/10,000 to <1/1000) | Frequency unknown*
Blood and lymphatic system disorders |  |  |  | Thrombocytopenia, Haemolytic anaemia
Immune system disorders |  |  |  | Anaphylactoid reaction
Psychiatric disorders |  |  |  | Anxiety Confusional state
Nervous system disorders |  | Headache Dizziness | Presyncope | Coma Transient ischaemic attack Paralysis Syncope Convulsion Loss of consciousness Dysarthria Paraesthesia Amnesia Somnolence Taste abnormality
Eye disorders |  |  |  | Blindness transient Visual disturbance Conjunctivitis Lacrimation increased Photopsia
Cardiac disorders |  |  | Bradycardia Tachycardia Extrasystoles | Cardiac arrest Myocardial infarction Cardiac failure Angina pectoris Arrhythmia Ventricular or atrial fibrillation Atrioventricular block Palpitations Cyanosis
Vascular disorders |  | Hypertension | Hypotension | Circulatory collapse or shock Hot flush Flushing Pallor
Respiratory, thoracic and mediastinal disorders |  | Dyspnoea |  | Respiratory arrest Acute respiratory distress syndrome (ARDS) Pulmonary oedema Laryngeal oedema Pharyngeal oedema Bronchospasm Asthma Cough Hyperventilation Pharynx discomfort Laryngeal discomfort Rhinitis Dysphonia
Gastrointestinal disorders |  | Nausea Vomiting |  | Diarrhoea Abdominal pain Salivary hypersecretion Dysphagia Salivary gland enlargement
Skin and subcutaneous tissue disorders |  | Erythema Urticaria Pruritus | Rash | Acute generalized exanthematous pustulosis Angioedema Cold sweat Sweating increased
Musculoskeletal and connective tissue disorder |  |  | Back pain | Arthralgia
Renal and urinary disorders |  |  |  | Renal failure
General disorders and administration site conditions | Feeling hot | Chest pain Injection site warmth and pain | Asthenia Rigors Pyrexia | Injection site reaction** Coldness local Fatigue Malaise Thirst
Investigations |  |  | Blood creatinine increased | Electrocardiogram ST segment elevation Electrocardiogram abnormal
* Since the reactions were not observed during clinical trials with 4515 patients, best estimate is that their relative occurrence is rare (≥1/10,000 to <1/1000).
The most appropriate MedDRA term is used to describe a certain reaction and its symptoms and related conditions.
** Injection site reactions comprise injection site pain and swelling. In the majority of cases they are due to extravasation of contrast medium. These reactions are usually transient and result in recovery without sequelae. Cases of extravasation with inflammation, skin necrosis and even development of compartment syndrome have been reported.

Coronary artery thrombosis and coronary artery embolism have been reported as a complication of coronary catheterization procedures.

Vasospasm and consequent ischaemia have been observed during intra-arterial injections of contrast medium, in particular after coronary and cerebral angiography often procedurally related and possibly triggered by the tip of the catheter or excess catheter pressure.

As with other iodinated contrast media, very rare cases of mucocutaneous syndromes, including Stevens-Johnson syndrome, toxic epidermal necrolysis (Lyell syndrome) and erythema multiforme, have been reported following the administration of Iomeprol injection.

Paediatric patients

There is limited experience with paediatric patients. The clinical trial paediatric safety database comprises 167 patients.

The Iomeprol safety profile is similar in children and adults.

4.8.2 Administration to body cavities

After injection of an iodinated contrast media in body cavities, contrast media are slowly absorbed from the area of administration into the systemic circulation and subsequently cleared by renal elimination.

Blood amylase increased is common following ERCP. Very rare cases of pancreatitis have been described.

The reactions reported in cases of arthrography and fistulography usually represent irritative manifestations superimposed on pre-existing conditions of tissue inflammation.

Hypersensitivity reactions are rare, generally mild and in the form of skin reactions. However, the possibility of severe anaphylactoid reactions cannot be excluded.

As with other iodinated contrast media, pelvic pain and malaise may occur after hysterosalpingography.

Reporting of suspected adverse reactions
Reporting suspected adverse reactions after authorisation of the medicinal product is important. It allows continued monitoring of the benefit/risk balance of the medicinal product. Healthcare professionals are asked to report any suspected adverse reactions via the Yellow Card Scheme
Website: www.mhra.gov.uk/yellowcard or search for MHRA Yellow Card in the Google Play or Apple App Store.

4.9 Overdose

The effects of overdose on the pulmonary and cardiovascular systems may become life-threatening. Treatment consists of support of the vital functions and prompt use of symptomatic therapy. Iomeprol does not bind to plasma or serum proteins and is therefore dialyzable.

5 PHARMACOLOGICAL PROPERTIES

5.1 Pharmacodynamic properties

ATC code: V08AB10

Iomeprol is a low osmolality, non-ionic organic molecule with radio-opacity conferred by an iodine content of 49% of the molecular weight. It is formulated for use as an intravascular/intracavitary contrast medium in concentrations of up to 400mg iodine per ml. Even at this concentration the low viscosity allows delivery of high doses through thin catheters.

5.2 Pharmacokinetic properties

The pharmacokinetics of intravascularly administered iomeprol are similar to those of other iodinated contrast media and conform to a two-compartment model with a rapid distribution and a slower elimination phase. In healthy subjects, the mean distribution and elimination half-lives of iomeprol were 0.5 hours and 1.9 hours respectively.

Distribution volume is similar to that of extra cellular fluid. There is no significant serum protein binding and iomeprol is not metabolized.

Elimination is almost exclusively through the kidneys (90% of the dose recovered in the urine within 96 hours of its administration) and is rapid (50% of an intravascularly administered dose within 2 hours).

5.3 Preclinical Safety Data

Pre-clinical data reveal no special hazard for humans based on conventional studies of safety pharmacology, repeated dose toxicity, genotoxicity, toxicity to reproduction.

Results from studies in rats, mice and dogs demonstrate that iomeprol has an acute intravenous or intra-arterial toxicity similar to that of the other non ionic contrast media, as well as a good systemic tolerability after repeated intravenous administrations in rats and dogs.

6. PHARMACEUTICAL PARTICULARS

6.1 List of excipients

trometamol
hydrochloric acid
water for injection

6.2 Incompatibilities

In the absence of compatibility studies, this medicinal product must not be mixed with other medicinal products. No other drug should be mixed with the contrast medium.

6.3 Shelf Life

Five years

6.4 Special precautions for storage

Store below 30°C
Protect from light

6.5 Nature and contents of containers

Colourless Type I or Type II glass bottles with rubber/aluminium cap.
Quantities of 20, 30, 50, 75, 100, 150, 200 or 250 ml of solution.

6.6 Special precautions for disposal and other handling

Bottles containing contrast media solution are not intended for the withdrawal of multiple doses. The rubber stopper should never be pierced more than once. The use of proper withdrawal cannulas for piercing the stopper and drawing up the contrast medium is recommended.

Before use, examine the product to assure that the container and closure have not been damaged. Do not use the solution if it is discolored or particulate matter is present.

The contrast medium should not be drawn into the syringe until immediately before use. Withdrawal of contrast agents from their containers should be accomplished under aseptic conditions with sterile syringes. Sterile techniques must be used with any spinal puncture or intravascular injection, and with catheters and guidewires. If non-disposable equipment is used, scrupulous care should be taken to prevent residual contamination with traces of cleansing agents.

It is desirable that solutions of contrast media for intravascular and intrathecal use should be at body temperature when injected.

Any residue of contrast medium in the syringe must be discarded. Solutions not used in one examination session or waste material, such as the connecting tubes, should be disposed in accordance with local requirements.

7. MARKETING AUTHORISATION HOLDER

Bracco UK Ltd
Magdalen Centre
The Oxford Science Park
Oxford, OX4 4GA
United Kingdom

8. MARKETING AUTHORISATION NUMBER

18920/0006

9. DATE OF FIRST AUTHORISATION/RENEWAL OF AUTHORISATION

11 December 1992 / 29 December 1998

10. DATE OF REVISION OF THE TEXT

19 January 2022

MEDICATION GUIDE

1. NAME OF THE MEDICINAL PRODUCT

Iomeron 300, solution for injection, multi-dose container

2. QUALITATIVE AND QUANTITATIVE COMPOSITION

Contains 61.24% w/v of Iomeprol equivalent to 30% iodine or 300 mg iodine/ml.

For the full list of excipients, see section 6.1.

3. PHARMACEUTICAL FORM

Solution for injection.
A clear colourless to pale yellow solution supplied in glass multi-dose container.

4. CLINICAL PARTICULARS

4.1 Therapeutic indications

X-ray contrast medium used for computed tomography enhancement, including CTA (CT Angiography).

4.2 Posology and method of administration

brain |  | adults | 50 - 150ml
 |  | children | *
body |  | adults | 40 - 150ml max 250ml
 |  | children | *
* According to body size and age

In elderly patients the lowest effective dose should be used.

4.3 Contraindications

Hypersensitivity to the active substance or any of the excipients.

4.4 Special warnings and special precautions for use

In consideration of possible complications, the patient should be kept under observation for at least 30 minutes after the examination.

Extreme caution during injection of contrast media is necessary to avoid extravasation.

A normal diet should be maintained until the patient refrains from eating 2 hours before the procedure.

Hydration
Any severe disorders of water and electrolyte balance must be corrected prior to administration. Adequate hydration must be ensured particularly in patients with diabetes mellitus, polyuria, oliguria and hyperuricaemia; also in babies, small children and the elderly. Rehydration prior to use of Iomeprol is recommended in patients with sickle cell disease.

Special population
Hypersensitivity to iodinated contrast media, allergic predisposition
A positive history of allergy, asthma or untoward reaction during previous similar investigations indicates a need for extra caution since, as with other contrast media, this product may provoke anaphylaxis or other manifestations of allergy with nausea, vomiting, dyspnoea, erythema, urticaria and hypotension. The benefits should clearly outweigh the risks in such patients and appropriate resuscitative measures should be immediately available. The primary treatments are as follows:

Effect | Major Symptoms | Primary Treatment
Vasomotor effect | warmth nausea/vomiting | reassurance
Cutaneous | scattered hives severe urticaria | H1-antihistamines H2-antihistamines
Bronchospastic | wheezing | oxygen Beta-2-agonist inhalers
Anaphylactoid | angioedema | oxygen
reaction | urticaria bronchospasm hypotension | iv fluids adrenergics (iv epinephrine) Inhaled beta-2-adrenergics
 |  | antihistamines (H1-and H2- blockers) corticosteroids
Hypotensive | hypotension | iv fluids
Vagal reaction | hypotension bradycardia | iv fluids iv atropine

From: Bush WH; The Contrast Media Manual; Katzburg RW Ed.; Williams and Wilkins; Baltimore 1992; Chapter 2 p 23

The risk of bronchospasm-inducing reactions in asthmatic patients is higher after contrast media administration, especially in patients taking beta-blockers.

Hypersensitivity testing
In patients with suspected or known hypersensitivity to contrast media, sensitivity test doses are not recommended, as severe or fatal reactions to contrast media are not predictable from sensitivity test.

Myelomatosis or paraproteinaemias are conditions predisposing to renal impairment following CM administration. The benefits of the use of a contrast-enhanced procedure should be carefully weighed against the possible risk. Adequate hydration and monitoring of renal function are recommended after CM administration.

Cardiovascular diseases
Care should be taken in patients with severe cardiac disease particularly heart failure and coronary artery disease. Cardiac manifestations may include pulmonary oedema, haemodynamic changes, ischaemic ECG changes and arrhythmias. In severe, chronic hypertension the risk of renal damage following administration of a contrast medium is increased.

The product should be used with caution in patients with hyperthyroidism or goitre. Use may interfere with thyroid function tests.

The administration of iodinated contrast media may aggravate myasthenia signs and symptoms.

CNS Disorders
Particular care is needed in patients with acute cerebral infarction, acute intracranial haemorrhage and any conditions involving damage to the blood brain barrier, brain oedema or acute demyelination. Convulsive seizures are more likely in patients with intracranial tumours or metastases or with a history of epilepsy.

Neurological symptoms related to cerebrovascular diseases, intracranial tumours/metastases or degenerative or inflammatory pathologies may be exacerbated.

There is an increased risk of transient neurological complications in patients with symptomatic cerebrovascular disease eg stroke, transient ischaemic attacks. Cerebral ischaemic phenomena may be caused by intravascular injection.

Anticonvulsant therapy should not be discontinued.

In acute and chronic alcoholism the increase in blood brain barrier permeability facilitates the passage of the contrast medium into cerebral tissue possibly leading to CMS disorders. There is a possibility of a reduced seizure threshold in alcoholics.

In patients with a drug addiction there is also the possibility of a reduced seizure threshold.

Patients with phaeochromocytoma may develop severe, occasionally uncontrollable hypertensive crises during intravascular administration. Premedication with an alpha and beta receptor-blocker is recommended in these patients. Pronounced excitement, anxiety and pain can cause side effects or intensify reaction to the contrast medium. A sedative may be given.

Renal failure
In patients with moderate to severe impairment of renal function, attention should be paid to renal function parameters, in particular before re-examining the patient with a contrast media.
Preventive measures include:

- identification of high-risk patients;
- ensuring adequate hydration before CM administration, preferably by maintaining i.v. infusion before and during the procedure and until the CM has been cleared by the kidneys;
- avoiding whenever possible, the administration of nephrotoxic drugs or major surgery or procedure such as renal angioplasty, until the CM has been cleared;

A combination of severe hepatic and renal impairment delays excretion of the contrast medium therefore such patients should not be examined unless absolutely necessary.

Diabetes mellitus
Care should be taken in renal impairment and diabetes. In these patients it is important to maintain hydration in order to minimise deterioration in renal function.
The presence of renal damage in diabetic patients is one of the factors predisposing to renal impairment following contrast media administration. This may precipitate lactic acidosis in patients who are taking metformin (see section 4.5 - Interaction with medicaments and other forms of interaction).

Children:
Infants up to 1 year, especially the new-born, are particularly susceptible to electrolyte imbalance and haemodynamic alterations. Care should be taken regarding the dosage used.
Transient hypothyroidism may occur in neonates when the mother or the neonate has received an
iodinated contrast agent. Thyroid function tests (usually TSH and T4) are recommended in neonates
7-10 days and 1 month after exposure to Iomeron especially in preterm neonates.
Elderly:
The elderly are at special risk of reactions due to reduced physiological functions, especially when high dosage of contrast media is used. A combination of neurological disturbances and vascular pathologies present a serious complication. The probability of acute renal insufficiencies is higher in these people.

Intravascular administration should be performed if possible with the patient lying down. The patient should be kept in this position and closely observed for at least 30 minutes after the procedure since the majority of severe incidents occur with this time.

4.5 Interaction with other medicinal products and other forms of interaction

Use of the product may interfere with tests for thyroid function. Vasopressor agents should not be administered prior to Iomeprol.

Treatment with drugs that lower the seizure threshold such as certain neuroleptics (MAO inhibitors, tricyclic antidepressants), analeptics, and anti-emetics and phenothiazine derivatives should be discontinued 48 hours before the examination. Treatment should not be resumed until 24 hours post-procedure.

It has been reported that cardiac and/or hypertensive patients under treatment with diuretics, ACE-inhibitors, and/or beta blocking agents are at higher risk of adverse reactions when administered iodinated contrast media.

Beta-blockers may impair the response to treatment of bronchospasm induced by contrast medium.

Patients with normal renal function can continue to take metformin normally. In diabetic patients with diabetic nephropathy, under treatment with metformin and with moderate renal impairment, metformin should be stopped at the time of, or prior to the procedure and withheld for 48 hours subsequent to the procedure and reinstituted only after renal function has been re-evaluated and found to be normal In emergency patients in whom renal function is either impaired or unknown, the physician shall weigh out risk and benefit of an examination with a contrast medium and take precautions. Metformin should be stopped from time of contrast medium administration. After the procedure the patient should be monitored for signs of lactic acidosis. Metformin should be restarted 48 hours after contrast medium if serum creatinine/eGFR is unchanged from the pre-imaging level.

Allergy-like reactions to contrast media are more frequent and may manifest as delayed reactions in patients treated with immuno-modulators, like Interleukin-2 (IL-2).

4.6 Fertility, pregnancy and lactation

Women of childbearing potential
Appropriate investigations and measures should be taken when exposing women of child-bearing potential to any X-ray examination, whether with or without contrast medium.

Pregnancy
Animal studies have not indicated any harmful effects with respect to the course of pregnancy or on the health of the unborn or neonate. The safety of Iomeprol in human pregnancy however has not been established. Therefore avoid in pregnancy unless there is no safer alternative.
Since, wherever possible, exposure to radiation should be avoided during pregnancy, the benefits of any X ray examination, whether with or without contrast material, should for this reason alone be carefully weighed against the possible risk.

Breastfeeding
No human data exist concerning the excretion of Iomeprol in breast milk. Animal studies have demonstrated that the excretion of Iomeprol in breast milk is similar to that of other contrast agents and that these compounds are only minimally absorbed by the gastrointestinal tract of the young. Adverse effects on the nursing infant are therefore unlikely to occur.

Stopping breastfeeding is unnecessary.

4.7 Effects on ability to drive and use machines

There is no known effect on the ability to drive and operate machines.

4.8 Undesirable effects

General

The use of iodinated contrast media may cause untoward side effects. They are usually mild to moderate and transient in nature. However, severe and life-threatening reactions sometimes leading to death have been reported. In most cases, reactions occur within minutes of dosing but at times reactions may occur at later time.

Anaphylaxis (anaphylactoid/hypersensitivity reactions) may manifest with various symptoms, and rarely does any one patient develop all the symptoms. Typically, in 1 to 15 min (but rarely after as long as 2 h), the patient complains of feeling abnormal, agitation, flushing, feeling hot, sweating increased, dizziness, increased lacrimation, rhinitis, palpitations, paresthesia, pruritus, sore throat and throat tightness, dysphagia, cough, sneezing, urticaria, erythema, mild localised oedema, angioneurotic oedema and dyspnoea due to glottic/laryngeal/pharyngeal oedema and/or spasm manifesting with wheezing, and bronchospasm.
Nausea, vomiting, abdominal pain, and diarrhoea are also reported.
These reactions, which can occur independently of the dose administered or the route of administration, may represent the first signs of circulatory collapse.
Administration of the contrast medium must be discontinued immediately and, if needed, appropriate specific treatment urgently initiated via venous access.
Severe reactions involving the cardiovascular system, such as vasodilatation, with pronounced hypotension, tachycardia, dyspnoea, agitation, cyanosis and loss of consciousness progressing to respiratory and/or cardiac arrest may result in death. These events can occur rapidly and require full and aggressive cardio-pulmonary resuscitation.
Primary circulatory collapse can occur as the only and/or initial presentation without respiratory symptoms or without other signs or symptoms outlined above.

The adverse reactions reported in clinical trials and from post-marketing surveillance are represented in the tables below by frequency and classified by MedDRA system organ class.

Within each frequency grouping, adverse reactions are presented in order of decreasing seriousness.

Adult patients involved in clinical trials with intravascular administration of Iomeprol were 4,515.

Adults
System Organ Class | Adverse Reactions
System Organ Class | Clinical Trials |  |  | Post-marketing Surveillance
System Organ Class | Common (≥1/100 t o <1/10) | Uncommon (≥1/1000 to <1/100) | Rare (≥1/10,000 to <1/1000) | Frequency unknown*
Blood and lymphatic system disorders |  |  |  | Thrombocytopenia, Haemolytic anaemia
Immune system disorders |  |  |  | Anaphylactoid reaction
Psychiatric disorders |  |  |  | Anxiety Confusional state
Nervous system disorders |  | Headache Dizziness | Presyncope | Coma Transient ischaemic attack Paralysis Syncope Convulsion Loss of consciousness Dysarthria Paraesthesia Amnesia Somnolence Taste abnormality
Eye disorders |  |  |  | Blindness transient Visual disturbance Conjunctivitis Lacrimation increased Photopsia
Cardiac disorders |  |  | Bradycardia Tachycardia | Cardiac arrest Myocardial infarction Cardiac failure Angina pectoris Arrhythmia Ventricular or atrial fibrillation Atrioventricular block Extrasystoles Palpitations Cyanosis
Vascular disorders |  | Hypertension | Hypotension | Circulatory collapse or shock Hot flush Flushing Pallor
Respiratory, thoracic and mediastinal disorders |  | Dyspnoea |  | Respiratory arrest Acute respiratory distress syndrome (ARDS) Pulmonary oedema Laryngeal oedema Pharyngeal oedema Bronchospasm Asthma Cough Hyperventilation Pharynx discomfort Laryngeal discomfort Rhinitis Dysphonia
Gastrointestinal disorders |  | Nausea Vomiting |  | Diarrhoea Abdominal pain Salivary hypersecretion Dysphagia Salivary gland enlargement
Skin and subcutaneous tissue disorders |  | Erythema Urticaria Pruritus | Rash | Acute generalized exanthematous pustulosis Angioedema Cold sweat Sweating increased
Musculoskeletal and connective tissue disorder |  |  | Back pain | Arthralgia
Renal and urinary disorders |  |  |  | Renal failure
General disorders and administration site conditions | Feeling hot | Chest pain Injection site warmth and pain | Asthenia Rigors Pyrexia | Injection site reaction** Coldness local Fatigue Malaise Thirst
Investigations |  |  | Blood creatinine increased | Electrocardiogram ST segment elevation Electrocardiogram abnormal
* Since the reactions were not observed during clinical trials with 4515 patients, best estimate is that their relative occurrence is rare (≥1/10,000 to <1/1000).
The most appropriate MedDRA term is used to describe a certain reaction and its symptoms and related conditions.
** Injection site reactions comprise injection site pain and swelling. In the majority of cases they are due to extravasation of contrast medium. These reactions are usually transient and result in recovery without sequelae. Cases of extravasation with inflammation, skin necrosis and even development of compartment syndrome have been reported.

As with other iodinated contrast media, very rare cases of mucocutaneous syndromes, including Stevens-Johnson syndrome, toxic epidermal necrolysis (Lyell syndrome) and erythema multiforme, have been reported following the administration of Iomeprol injection.

Paediatric patients

There is limited experience with paediatric patients. The clinical trial paediatric safety database comprises 167 patients.

The Iomeprol safety profile is similar in children and adults.

Reporting of suspected adverse reactions
Reporting suspected adverse reactions after authorisation of the medicinal product is important. It allows continued monitoring of the benefit/risk balance of the medicinal product. Healthcare professionals are asked to report any suspected adverse reactions via the Yellow Card Scheme
Website: www.mhra.gov.uk/yellowcard or search for MHRA Yellow Card in the Google Play or Apple App Store.

4.9 Overdose

The effects of overdose on the pulmonary and cardiovascular systems may become life-threatening. Treatment consists of support of the vital functions and prompt use of symptomatic therapy. Iomeprol does not bind to plasma or serum proteins and is therefore dialyzable.

5 PHARMACOLOGICAL PROPERTIES

5.1 Pharmacodynamic properties

ATC code: V08AB10

Iomeprol is a low osmolality, non-ionic organic molecule with radio-opacity conferred by an iodine content of 49% of the molecular weight. It is formulated for use as an intravascular/intracavitary/ intrathecal contrast medium in concentrations of up to 400mg iodine per ml. Even at this concentration the low viscosity allows delivery of high doses through thin catheters.

5.2 Pharmacokinetic properties

The pharmacokinetics of intravascularly administered Iomeprol are similar to those of other iodinated contrast media and conform to a two-compartment model with a rapid distribution and a slower elimination phase. In healthy subjects, the mean distribution and elimination half-lives of Iomeprol were 0.5 hours and 1.9 hours respectively.

Distribution volume is similar to that of extra cellular fluid. There is no significant serum protein binding and Iomeprol is not metabolized.

Elimination is almost exclusively through the kidneys (90% of the dose recovered in the urine within 96 hours of its administration) and is rapid (50% of an intravascularly administered dose within 2 hours).

5.3 Preclinical Safety Data

Pre-clinical data reveal no special hazard for humans based on conventional studies of safety pharmacology, repeated dose toxicity, genotoxicity, toxicity to reproduction.

Results from studies in rats, mice and dogs demonstrate that Iomeprol has an acute intravenous or intra-arterial toxicity similar to that of the other non ionic contrast media, as well as a good systemic tolerability after repeated intravenous administrations in rats and dogs.

6. PHARMACEUTICAL PARTICULARS

6.1 List of excipients

trometamol
hydrochloric acid
water for injection

6.2 Incompatibilities

In the absence of compatibility studies, this medicinal product must not be mixed with other medicinal products.

6.3 Shelf Life

Five years
The maximum use time after a bottle stopper has been pierced is 10 hours.

6.4 Special precautions for storage

Store below 30°C
Protect from light

6.5 Nature and contents of container

Colourless type I or type II glass bottles with chlorobutyl or bromobutyl rubber stopper/aluminium cap containing 500 ml of solution.
Boxes of 1, 5 and 6 bottles.

6.6 Special precautions for disposal and other handling

Before use, examine the product to assure that the container and closure have not been damaged. Do not use the solution if it is discolored or particulate matter is present. The stopper should be pierced only once. The use of proper withdrawal cannulas for piercing the stopper and drawing up the contrast medium is recommended.
Multi-dose containers should be used only in conjunction with an automatic injector which has been approved for multipatient use.
After each patient, the connector between the injector and the patient should be replaced. All other devices should be replaced following the injector manufacturer’s instructions. In any case, strictly follow the manufacturer’s instructions.
Any unused product or waste material should be disposed of in accordance with local requirements.

7. MARKETING AUTHORISATION HOLDER

Bracco UK Ltd
Magdalen Centre
The Oxford Science Park
Oxford, OX4 4GA
United Kingdom

8. MARKETING AUTHORISATION NUMBER

PL 18920/0041

9. DATE OF FIRST AUTHORISATION/RENEWAL OF AUTHORISATION

14/11/2018

10. DATE OF REVISION OF THE TEXT

12/11/2021

MEDICATION GUIDE

1. NAME OF THE MEDICINAL PRODUCT

Iomeron 350, solution for injection, multi-dose container

2. QUALITATIVE AND QUANTITATIVE COMPOSITION

Contains 71.44% w/v of Iomeprol equivalent to 35% iodine or 350 mg iodine/ml.

For the full list of excipients, see section 6.1.

3. PHARMACEUTICAL FORM

Solution for injection.
A clear colourless to pale yellow solution supplied in glass multi-dose container.

4. CLINICAL PARTICULARS

4.1 Therapeutic indications

X-ray contrast medium used for computed tomography enhancement, including CTA (CT Angiography).

4.2 Posology and method of administration

brain |  | adults | 50 - 150ml
 |  | children | *
body |  | adults | 40 - 150ml max 250ml
 |  | children | *
* According to body size and age

In elderly patients the lowest effective dose should be used.

4.3 Contraindications

Hypersensitivity to the active substance or any of the excipients.

4.4 Special warnings and special precautions for use

In consideration of possible complications, the patient should be kept under observation for at least 30 minutes after the examination.

Extreme caution during injection of contrast media is necessary to avoid extravasation.

A normal diet should be maintained until the patient refrains from eating 2 hours before the procedure.

Hydration
Any severe disorders of water and electrolyte balance must be corrected prior to administration. Adequate hydration must be ensured particularly in patients with diabetes mellitus, polyuria, oliguria and hyperuricaemia; also in babies, small children and the elderly. Rehydration prior to use of Iomeprol is recommended in patients with sickle cell disease.

Special population
Hypersensitivity to iodinated contrast media, allergic predisposition
A positive history of allergy, asthma or untoward reaction during previous similar investigations indicates a need for extra caution since, as with other contrast media, this product may provoke anaphylaxis or other manifestations of allergy with nausea, vomiting, dyspnoea, erythema, urticaria and hypotension. The benefits should clearly outweigh the risks in such patients and appropriate resuscitative measures should be immediately available. The primary treatments are as follows:

Effect | Major Symptoms | Primary Treatment
Vasomotor effect | warmth nausea/vomiting | reassurance
Cutaneous | scattered hives severe urticaria | H1-antihistamines H2-antihistamines
Bronchospastic | wheezing | oxygen Beta-2-agonist inhalers
Anaphylactoid | angioedema | oxygen
reaction | urticaria bronchospasm hypotension | iv fluids adrenergics (iv epinephrine) Inhaled beta-2-adrenergics
 |  | antihistamines (H1-and H2- blockers) corticosteroids
Hypotensive | hypotension | iv fluids
Vagal reaction | hypotension bradycardia | iv fluids iv atropine

From: Bush WH; The Contrast Media Manual; Katzburg RW Ed.; Williams and Wilkins; Baltimore 1992; Chapter 2 p 23

The risk of bronchospasm-inducing reactions in asthmatic patients is higher after contrast media administration, especially in patients taking beta-blockers.

Hypersensitivity testing
In patients with suspected or known hypersensitivity to contrast media, sensitivity test doses are not recommended, as severe or fatal reactions to contrast media are not predictable from sensitivity test.

Myelomatosis or paraproteinaemias are conditions predisposing to renal impairment following CM administration. The benefits of the use of a contrast-enhanced procedure should be carefully weighed against the possible risk. Adequate hydration and monitoring of renal function are recommended after CM administration.

Cardiovascular diseases
Care should be taken in patients with severe cardiac disease particularly heart failure and coronary artery disease. Cardiac manifestations may include pulmonary oedema, haemodynamic changes, ischaemic ECG changes and arrhythmias. In severe, chronic hypertension the risk of renal damage following administration of a contrast medium is increased.

The product should be used with caution in patients with hyperthyroidism or goitre. Use may interfere with thyroid function tests.

The administration of iodinated contrast media may aggravate myasthenia signs and symptoms.

CNS Disorders
Particular care is needed in patients with acute cerebral infarction, acute intracranial haemorrhage and any conditions involving damage to the blood brain barrier, brain oedema or acute demyelination. Convulsive seizures are more likely in patients with intracranial tumours or metastases or with a history of epilepsy.

Neurological symptoms related to cerebrovascular diseases, intracranial tumours/metastases or degenerative or inflammatory pathologies may be exacerbated.

There is an increased risk of transient neurological complications in patients with symptomatic cerebrovascular disease eg stroke, transient ischaemic attacks. Cerebral ischaemic phenomena may be caused by intravascular injection.

Anticonvulsant therapy should not be discontinued.

In acute and chronic alcoholism the increase in blood brain barrier permeability facilitates the passage of contrast medium into cerebral tissue possibly leading to CNS disorders. There is a possibility of a reduced seizure threshold in alcoholics.

In patients with a drug addiction there is also the possibility of a reduced seizure threshold.

Patients with phaeochromocytoma may develop severe, occasionally uncontrollable hypertensive crises during intravascular administration. Premedication with an alpha and beta receptor-blocker is recommended in these patients. Pronounced excitement, anxiety and pain can cause side effects or intensify reaction to the contrast medium. A sedative may be given.

Renal failure
In patients with moderate to severe impairment of renal function, attention should be paid to renal function parameters, before re-examining the patient with a contrast media.
Preventive measures include:

- identification of high-risk patients;
- ensuring adequate hydration before CM administration, preferably by maintaining i.v. infusion before and during the procedure and until the CM has been cleared by the kidneys;
- avoiding whenever possible, the administration of nephrotoxic drugs or major surgery or procedure such as renal angioplasty, until the CM has been cleared;

A combination of severe hepatic and renal impairment delays excretion of the contrast medium therefore such patients should not be examined unless absolutely necessary.

Diabetes mellitus
Care should be taken in renal impairment and diabetes. In these patients it is important to maintain hydration in order to minimise deterioration in renal function.
The presence of renal damage in diabetic patients is one of the factors predisposing to renal impairment following contrast media administration. This may precipitate lactic acidosis in patients who are taking metformin (see section 4.5 - Interaction with medicaments and other forms of interaction).

Children: Infants up to 1 year, especially the new-born, are particularly susceptible to electrolyte imbalance and haemodynamic alterations. Care should be taken regarding the dosage used.
Transient hypothyroidism may occur in neonates when the mother or the neonate has received an
iodinated contrast agent. Thyroid function tests (usually TSH and T4) are recommended in neonates
7-10 days and 1 month after exposure to Iomeron especially in preterm neonates.

Elderly:
The elderly are at special risk of reactions due to reduced physiological functions, especially when high dosage of contrast media is used. A combination of neurological disturbances and vascular pathologies present a serious complication. The probability of acute renal insufficiencies is higher in these people.

Intravascular administration should be performed if possible with the patient lying down. The patient should be kept in this position and closely observed for at least 30 minutes after the procedure since the majority of severe incidents occur with this time.

4.5 Interaction with other medicinal products and other forms of interaction

Use of the product may interfere with tests for thyroid function. Vasopressor agents should not be administered prior to Iomeprol.

Treatment with drugs that lower the seizure threshold such as certain neuroleptics (MAO inhibitors, tricyclic antidepressants), analeptics, and anti-emetics and phenothiazine derivatives should be discontinued 48 hours before the examination. Treatment should not be resumed until 24 hours post-procedure.

It has been reported that cardiac and/or hypertensive patients under treatment with diuretics, ACE-inhibitors, and/or beta blocking agents are at higher risk of adverse reactions when administered iodinated contrast media.

Beta-blockers may impair the response to treatment of bronchospasm induced by contrast medium.

Patients with normal renal function can continue to take metformin normally. In diabetic patients with diabetic nephropathy, under treatment with metformin and with moderate renal impairment, metformin should be stopped at the time of, or prior to the procedure and withheld for 48 hours subsequent to the procedure and reinstituted only after renal function has been re-evaluated and found to be normal In emergency patients in whom renal function is either impaired or unknown, the physician shall weigh out risk and benefit of an examination with a contrast medium and take precautions. Metformin should be stopped from time of contrast medium administration. After the procedure the patient should be monitored for signs of lactic acidosis. Metformin should be restarted 48 hours after contrast medium if serum creatinine/eGFR is unchanged from the pre-imaging level.

Allergy-like reactions to contrast media are more frequent and may manifest as delayed reactions in patients treated with immuno-modulators, like Interleukin-2 (IL-2).

4.6 Fertility, pregnancy and lactation

Women of childbearing potential
Appropriate investigations and measures should be taken when exposing women of child-bearing potential to any X-ray examination, whether with or without contrast medium.

Pregnancy
Animal studies have not indicated any harmful effects with respect to the course of pregnancy or on the health of the unborn or neonate. The safety of Iomeprol in human pregnancy however has not been established. Therefore avoid in pregnancy unless there is no safer alternative.
Since, wherever possible, exposure to radiation should be avoided during pregnancy, the benefits of any X ray examination, whether with or without contrast material, should for this reason alone be carefully weighed against the possible risk.

Breastfeeding
No human data exist concerning the excretion of Iomeprol in breast milk. Animal studies have demonstrated that the excretion of Iomeprol in breast milk is similar to that of other contrast agents and that these compounds are only minimally absorbed by the gastrointestinal tract of the young. Adverse effects on the nursing infant are therefore unlikely to occur.
Stopping breastfeeding is unnecessary.

4.7 Effects on ability to drive and use machines

There is no known effect on the ability to drive and operate machines.

4.8 Undesirable effects

General

The use of iodinated contrast media may cause untoward side effects. They are usually mild to moderate and transient in nature. However, severe and life-threatening reactions sometimes leading to death have been reported. In most cases, reactions occur within minutes of dosing but at times reactions may occur at later time.

Anaphylaxis (anaphylactoid/hypersensitivity reactions) may manifest with various symptoms, and rarely does any one patient develop all the symptoms. Typically, in 1 to 15 min (but rarely after as long as 2 h), the patient complains of feeling abnormal, agitation, flushing, feeling hot, sweating increased, dizziness, increased lacrimation, rhinitis, palpitations, paresthesia, pruritus, sore throat and throat tightness, dysphagia, cough, sneezing, urticaria, erythema, mild localised oedema, angioneurotic oedema and dyspnoea due to glottic/laryngeal/pharyngeal oedema and/or spasm manifesting with wheezing, and bronchospasm.
Nausea, vomiting, abdominal pain, and diarrhoea are also reported.
These reactions, which can occur independently of the dose administered or the route of administration, may represent the first signs of circulatory collapse.
Administration of the contrast medium must be discontinued immediately and, if needed, appropriate specific treatment urgently initiated via venous access.
Severe reactions involving the cardiovascular system, such as vasodilatation, with pronounced hypotension, tachycardia, dyspnoea, agitation, cyanosis and loss of consciousness progressing to respiratory and/or cardiac arrest may result in death. These events can occur rapidly and require full and aggressive cardio-pulmonary resuscitation.
Primary circulatory collapse can occur as the only and/or initial presentation without respiratory symptoms or without other signs or symptoms outlined above.

The adverse reactions reported in clinical trials among 4,903 adult patients and from post-marketing surveillance are represented in the tables below by frequency and classified by MedDRA system organ class.

Within each frequency grouping, adverse reactions are presented in order of decreasing seriousness.

Adult patients involved in clinical trials with intravascular administration of Iomeprol were 4,515.

Adults
System Organ Class | Adverse Reactions
System Organ Class | Clinical Trials |  |  | Post-marketing Surveillance
System Organ Class | Common (≥1/100 t o <1/10) | Uncommon (≥1/1000 to <1/100) | Rare (≥1/10,000 to <1/1000) | Frequency unknown*
Blood and lymphatic system disorders |  |  |  | Thrombocytopenia, Haemolytic anaemia
Immune system disorders |  |  |  | Anaphylactoid reaction
Psychiatric disorders |  |  |  | Anxiety Confusional state
Nervous system disorders |  | Headache Dizziness | Presyncope | Coma Transient ischaemic attack Paralysis Syncope Convulsion Loss of consciousness Dysarthria Paraesthesia Amnesia Somnolence Taste abnormality
Eye disorders |  |  |  | Blindness transient Visual disturbance Conjunctivitis Lacrimation increased Photopsia
Cardiac disorders |  |  | Bradycardia Tachycardia | Cardiac arrest Myocardial infarction Cardiac failure Angina pectoris Arrhythmia Ventricular or atrial fibrillation Atrioventricular block Extrasystoles Palpitations Cyanosis
Vascular disorders |  | Hypertension | Hypotension | Circulatory collapse or shock Hot flush Flushing Pallor
Respiratory, thoracic and mediastinal disorders |  | Dyspnoea |  | Respiratory arrest Acute respiratory distress syndrome (ARDS) Pulmonary oedema Laryngeal oedema Pharyngeal oedema Bronchospasm Asthma Cough Hyperventilation Pharynx discomfort Laryngeal discomfort Rhinitis Dysphonia
Gastrointestinal disorders |  | Nausea Vomiting |  | Diarrhoea Abdominal pain Salivary hypersecretion Dysphagia Salivary gland enlargement
Skin and subcutaneous tissue disorders |  | Erythema Urticaria Pruritus | Rash | Acute generalized exanthematous pustulosis Angioedema Cold sweat Sweating increased
Musculoskeletal and connective tissue disorder |  |  | Back pain | Arthralgia
Renal and urinary disorders |  |  |  | Renal failure
General disorders and administration site conditions | Feeling hot | Chest pain Injection site warmth and pain | Asthenia Rigors Pyrexia | Injection site reaction** Coldness local Fatigue Malaise Thirst
Investigations |  |  | Blood creatinine increased | Electrocardiogram ST segment elevation Electrocardiogram abnormal
* Since the reactions were not observed during clinical trials with 4515 patients, best estimate is that their relative occurrence is rare (≥1/10,000 to <1/1000).
The most appropriate MedDRA term is used to describe a certain reaction and its symptoms and related conditions.
** Injection site reactions comprise injection site pain and swelling. In the majority of cases they are due to extravasation of contrast medium. These reactions are usually transient and result in recovery without sequelae. Cases of extravasation with inflammation, skin necrosis and even development of compartment syndrome have been reported.

As with other iodinated contrast media, very rare cases of mucocutaneous syndromes, including Stevens-Johnson syndrome, toxic epidermal necrolysis (Lyell syndrome) and erythema multiforme, have been reported following the administration of Iomeprol injection.

Paediatric patients

There is limited experience with paediatric patients. The clinical trial paediatric safety database comprises 167 patients.

The Iomeprol safety profile is similar in children and adults.

Reporting of suspected adverse reactions
Reporting suspected adverse reactions after authorisation of the medicinal product is important. It allows continued monitoring of the benefit/risk balance of the medicinal product. Healthcare professionals are asked to report any suspected adverse reactions via the Yellow Card Scheme
Website: www.mhra.gov.uk/yellowcard or search for MHRA Yellow Card in the Google Play or Apple App Store.

4.9 Overdose

The effects of overdose on the pulmonary and cardiovascular systems may become life-threatening. Treatment consists of support of the vital functions and prompt use of symptomatic therapy. Iomeprol does not bind to plasma or serum proteins and is therefore dialyzable.

5 PHARMACOLOGICAL PROPERTIES

5.1 Pharmacodynamic properties

ATC code: V08AB10

Iomeprol is a low osmolality, non-ionic organic molecule with radio-opacity conferred by an iodine content of 49% of the molecular weight. It is formulated for use as an intravascular/intracavitary/ intrathecal contrast medium in concentrations of up to 400mg iodine per ml. Even at this concentration the low viscosity allows delivery of high doses through thin catheters.

5.2 Pharmacokinetic properties

The pharmacokinetics of intravascularly administered Iomeprol are similar to those of other iodinated contrast media and conform to a two-compartment model with a rapid distribution and a slower elimination phase. In healthy subjects, the mean distribution and elimination half-lives of Iomeprol were 0.5 hours and 1.9 hours respectively.

Distribution volume is similar to that of extra cellular fluid. There is no significant serum protein binding and Iomeprol is not metabolized.

Elimination is almost exclusively through the kidneys (90% of the dose recovered in the urine within 96 hours of its administration) and is rapid (50% of an intravascularly administered dose within 2 hours).

5.3 Preclinical Safety Data

Pre-clinical data reveal no special hazard for humans based on conventional studies of safety pharmacology, repeated dose toxicity, genotoxicity, toxicity to reproduction.

Results from studies in rats, mice and dogs demonstrate that Iomeprol has an acute intravenous or intra-arterial toxicity similar to that of the other non ionic contrast media, as well as a good systemic tolerability after repeated intravenous administrations in rats and dogs.

6. PHARMACEUTICAL PARTICULARS

6.1 List of excipients

trometamol
hydrochloric acid
water for injection

6.2 Incompatibilities

In the absence of compatibility studies, this medicinal product must not be mixed with other medicinal products.

6.3 Shelf Life

Five years
The maximum use time after a bottle stopper has been pierced is 10 hours.

6.4 Special precautions for storage

Store below 30°C
Protect from light

6.5 Nature and contents of containers

Colourless type I or type II glass bottles with chlorobutyl or bromobutyl rubber stopper/aluminium cap containing 500 ml of solution.
Boxes of 1, 5 and 6 bottles.

6.6 Special precautions for disposal and other handling

Before use, examine the product to assure that the container and closure have not been damaged. Do not use the solution if it is discolored or particulate matter is present. The stopper should be pierced only once. The use of proper withdrawal cannulas for piercing the stopper and drawing up the contrast medium is recommended.
Multi-dose containers should be used only in conjunction with an automatic injector which has been approved for multipatient use.
After each patient, the connector between the injector and the patient should be replaced. All other devices should be replaced following the injector manufacturer’s instructions. In any case, strictly follow the manufacturer’s instructions.
Any unused product or waste material should be disposed of in accordance with local requirements.

7. MARKETING AUTHORISATION HOLDER

Bracco UK Ltd
Magdalen Centre
The Oxford Science Park
Oxford, OX4 4GA
United Kingdom

8. MARKETING AUTHORISATION NUMBER

PL 18920/0042

9. DATE OF FIRST AUTHORISATION/RENEWAL OF AUTHORISATION

14/11/2018

10. DATE OF REVISION OF THE TEXT

12/11/2021

MEDICATION GUIDE

1. NAME OF THE MEDICINAL PRODUCT

Iomeron 400, solution for injection, multi-dose container

2. QUALITATIVE AND QUANTITATIVE COMPOSITION

Contains 81.65% w/v of Iomeprol equivalent to 40% iodine or 400 mg iodine/ml.

For the full list of excipients, see section 6.1.

3. PHARMACEUTICAL FORM

Solution for injection.
A clear colourless to pale yellow solution supplied in glass multi-dose container.

4. CLINICAL PARTICULARS

4.1 Therapeutic indications

X-ray contrast medium used for computed tomography enhancement, including CTA (CT Angiography).

4.2 Posology and method of administration

computed tomography

body

adults

40 - 150ml max 250ml

children

*

* According to body size and age

In elderly patients the lowest effective dose should be used.

4.3 Contraindications

Hypersensitivity to the active substance or any of the excipients.

4.4 Special warnings and special precautions for use

In consideration of possible complications, the patient should be kept under observation for at least 30 minutes after the examination.

Extreme caution during injection of contrast media is necessary to avoid extravasation.

A normal diet should be maintained until the patient refrains from eating 2 hours before the procedure.

Hydration
Any severe disorders of water and electrolyte balance must be corrected prior to administration. Adequate hydration must be ensured particularly in patients with diabetes mellitus, polyuria, oliguria and hyperuricaemia; also in babies, small children and the elderly. Rehydration prior to use of Iomeprol is recommended in patients with sickle cell disease.

Special population
Hypersensitivity to iodinated contrast media, allergic predisposition
A positive history of allergy, asthma or untoward reaction during previous similar investigations indicates a need for extra caution since, as with other contrast media, this product may provoke anaphylaxis or other manifestations of allergy with nausea, vomiting, dyspnoea, erythema, urticaria and hypotension. The benefits should clearly outweigh the risks in such patients and appropriate resuscitative measures should be immediately available. The primary treatments are as follows:

Effect | Major Symptoms | Primary Treatment
Vasomotor effect | warmth nausea/vomiting | reassurance
Cutaneous | scattered hives severe urticaria | H1-antihistamines H2-antihistamines
Bronchospastic | wheezing | oxygen Beta-2-agonist inhalers
Anaphylactoid | angioedema | oxygen
reaction | urticaria bronchospasm hypotension | iv fluids adrenergics (iv epinephrine) Inhaled beta-2-adrenergics
 |  | antihistamines (H1-and H2- blockers) corticosteroids
Hypotensive | hypotension | iv fluids
Vagal reaction | hypotension bradycardia | iv fluids iv atropine

From: Bush WH; The Contrast Media Manual; Katzburg RW Ed.; Williams and Wilkins; Baltimore 1992; Chapter 2 p 23

The risk of bronchospasm-inducing reactions in asthmatic patients is higher after contrast media administration, especially in patients taking beta-blockers.

Hypersensitivity testing
In patients with suspected or known hypersensitivity to contrast media, sensitivity test doses are not recommended, as severe or fatal reactions to contrast media are not predictable from sensitivity test.

Myelomatosis or paraproteinaemias are conditions predisposing to renal impairment following CM administration. The benefits of the use of a contrast-enhanced procedure should be carefully weighed against the possible risk. Adequate hydration and monitoring of renal function are recommended after CM administration.

Cardiovascular diseases
Care should be taken in patients with severe cardiac disease particularly heart failure and coronary artery disease. Cardiac manifestations may include pulmonary oedema, haemodynamic changes, ischaemic ECG changes and arrhythmias. In severe, chronic hypertension the risk of renal damage following administration of a contrast medium is increased.

The product should be used with caution in patients with hyperthyroidism or goitre. Use may interfere with thyroid function tests.

The administration of iodinated contrast media may aggravate myasthenia signs and symptoms.

CNS Disorders
Particular care is needed in patients with acute cerebral infarction, acute intracranial haemorrhage and any conditions involving damage to the blood brain barrier, brain oedema or acute demyelination. Convulsive seizures are more likely in patients with intracranial tumours or metastases or with a history of epilepsy.

Neurological symptoms related to cerebrovascular diseases, intracranial tumours/metastases or degenerative or inflammatory pathologies may be exacerbated.

There is an increased risk of transient neurological complications in patients with symptomatic cerebrovascular disease eg stroke, transient ischaemic attacks. Cerebral ischaemic phenomena may be caused by intravascular injection.

Anticonvulsant therapy should not be discontinued.

In acute and chronic alcoholism the increase in blood brain barrier permeability facilitates the passage of the contrast medium into cerebral tissue possibly leading to CMS disorders. There is a possibility of a reduced seizure threshold in alcoholics

In patients with a drug addiction there is also the possibility of a reduced seizure threshold.

Patients with phaeochromocytoma may develop severe, occasionally uncontrollable hypertensive crises during intravascular administration. Premedication with an alpha and beta receptor-blocker is recommended in these patients. Pronounced excitement, anxiety and pain can cause side effects or intensify reaction to the contrast medium. A sedative may be given.

Renal failure
In patients with moderate to severe impairment of renal function, attention should be paid to renal function parameters, before re-examining the patient with a contrast media.
Preventive measures include:

- identification of high-risk patients;
- ensuring adequate hydration before CM administration, preferably by maintaining i.v. infusion before and during the procedure and until the CM has been cleared by the kidneys;
- avoiding whenever possible, the administration of nephrotoxic drugs or major surgery or procedure such as renal angioplasty, until the CM has been cleared;

A combination of severe hepatic and renal impairment delays excretion of the contrast medium therefore such patients should not be examined unless absolutely necessary.

Diabetes mellitus
Care should be taken in renal impairment and diabetes. In these patients it is important to maintain hydration in order to minimise deterioration in renal function.
The presence of renal damage in diabetic patients is one of the factors predisposing to renal impairment following contrast media administration. This may precipitate lactic acidosis in patients who are taking metformin (see section 4.5 - Interaction with medicaments and other forms of interaction).

Children: Infants up to 1 year, especially the newborn, are particularly susceptible to electrolyte imbalance and haemodynamic alterations. Care should be taken regarding the dosage used.
Transient hypothyroidism may occur in neonates when the mother or the neonate has received an
iodinated contrast agent. Thyroid function tests (usually TSH and T4) are recommended in neonates
7-10 days and 1 month after exposure to Iomeron especially in preterm neonates.

Elderly:
The elderly are at special risk of reactions due to reduced physiological functions, especially when high dosage of contrast media is used. A combination of neurological disturbances and vascular pathologies present a serious complication. The probability of acute renal insufficiencies is higher in these people.

Intravascular administration should be performed if possible with the patient lying down. The patient should be kept in this position and closely observed for at least 30 minutes after the procedure since the majority of severe incidents occur with this time.

4.5 Interaction with other medicinal products and other forms of interaction

Use of the product may interfere with tests for thyroid function. Vasopressor agents should not be administered prior to Iomeprol.
Treatment with drugs that lower the seizure threshold such as certain neuroleptics (MAO inhibitors, tricyclic antidepressants), analeptics, and anti-emetics and phenothiazine derivatives should be discontinued 48 hours before the examination. Treatment should not be resumed until 24 hours post-procedure.

It has been reported that cardiac and/or hypertensive patients under treatment with diuretics, ACE-inhibitors, and/or beta blocking agents are at higher risk of adverse reactions when administered iodinated contrast media.

Beta-blockers may impair the response to treatment of bronchospasm induced by contrast medium.

Patients with normal renal function can continue to take metformin normally. In diabetic patients with diabetic nephropathy, under treatment with metformin and with moderate renal impairment, metformin should be stopped at the time of, or prior to the procedure and withheld for 48 hours subsequent to the procedure and reinstituted only after renal function has been re-evaluated and found to be normal In emergency patients in whom renal function is either impaired or unknown, the physician shall weigh out risk and benefit of an examination with a contrast medium and take precautions. Metformin should be stopped from time of contrast medium administration. After the procedure the patient should be monitored for signs of lactic acidosis. Metformin should be restarted 48 hours after contrast medium if serum creatinine/eGFR is unchanged from the pre-imaging level.

Allergy-like reactions to contrast media are more frequent and may manifest as delayed reactions in patients treated with immuno-modulators, like Interleukin-2 (IL-2).

4.6 Fertility, pregnancy and lactation

Women of childbearing potential
Appropriate investigations and measures should be taken when exposing women of child-bearing potential to any X-ray examination, whether with or without contrast medium.

Pregnancy
Animal studies have not indicated any harmful effects with respect to the course of pregnancy or on the health of the unborn or neonate. The safety of Iomeprol in human pregnancy however has not been established. Therefore avoid in pregnancy unless there is no safer alternative.
Since, wherever possible, exposure to radiation should be avoided during pregnancy, the benefits of any X ray examination, whether with or without contrast material, should for this reason alone be carefully weighed against the possible risk.

Breastfeeding
No human data exist concerning the excretion of Iomeprol in breast milk. Animal studies have demonstrated that the excretion of Iomeprol in breast milk is similar to that of other contrast agents and that these compounds are only minimally absorbed by the gastrointestinal tract of the young. Adverse effects on the nursing infant are therefore unlikely to occur.

Stopping breastfeeding is unnecessary.

4.7 Effects on ability to drive and use machines

There is no known effect on the ability to drive and operate machines.

4.8 Undesirable effects

General

The use of iodinated contrast media may cause untoward side effects. They are usually mild to moderate and transient in nature. However, severe and life-threatening reactions sometimes leading to death have been reported. In most cases, reactions occur within minutes of dosing but at times reactions may occur at later time.

Anaphylaxis (anaphylactoid/hypersensitivity reactions) may manifest with various symptoms, and rarely does any one patient develop all the symptoms. Typically, in 1 to 15 min (but rarely after as long as 2 h), the patient complains of feeling abnormal, agitation, flushing, feeling hot, sweating increased, dizziness, increased lacrimation, rhinitis, palpitations, paresthesia, pruritus, sore throat and throat tightness, dysphagia, cough, sneezing, urticaria, erythema, mild localised oedema, angioneurotic oedema and dyspnoea due to glottic/laryngeal/pharyngeal oedema and/or spasm manifesting with wheezing, and bronchospasm.
Nausea, vomiting, abdominal pain, and diarrhoea are also reported.
These reactions, which can occur independently of the dose administered or the route of administration, may represent the first signs of circulatory collapse.
Administration of the contrast medium must be discontinued immediately and, if needed, appropriate specific treatment urgently initiated via venous access.
Severe reactions involving the cardiovascular system, such as vasodilatation, with pronounced hypotension, tachycardia, dyspnoea, agitation, cyanosis and loss of consciousness progressing to respiratory and/or cardiac arrest may result in death. These events can occur rapidly and require full and aggressive cardio-pulmonary resuscitation.
Primary circulatory collapse can occur as the only and/or initial presentation without respiratory symptoms or without other signs or symptoms outlined above.

The adverse reactions reported in clinical trials among 4,903 adult patients and from post-marketing surveillance are represented in the tables below by frequency and classified by MedDRA system organ class.
Within each frequency grouping, adverse reactions are presented in order of decreasing seriousness.

Adult patients involved in clinical trials with intravascular administration of Iomeprol were 4,515.

Adults
System Organ Class | Adverse Reactions
System Organ Class | Clinical Trials |  |  | Post-marketing Surveillance
System Organ Class | Common (≥1/100 t o <1/10) | Uncommon (≥1/1000 to <1/100) | Rare (≥1/10,000 to <1/1000) | Frequency unknown*
Blood and lymphatic system disorders |  |  |  | Thrombocytopenia, Haemolytic anaemia
Immune system disorders |  |  |  | Anaphylactoid reaction
Psychiatric disorders |  |  |  | Anxiety Confusional state
Nervous system disorders |  | Headache Dizziness | Presyncope | Coma Transient ischaemic attack Paralysis Syncope Convulsion Loss of consciousness Dysarthria Paraesthesia Amnesia Somnolence Taste abnormality
Eye disorders |  |  |  | Blindness transient Visual disturbance Conjunctivitis Lacrimation increased Photopsia
Cardiac disorders |  |  | Bradycardia Tachycardia | Cardiac arrest Myocardial infarction Cardiac failure Angina pectoris Arrhythmia Ventricular or atrial fibrillation Atrioventricular block Extrasystoles Palpitations Cyanosis
Vascular disorders |  | Hypertension | Hypotension | Circulatory collapse or shock Hot flush Flushing Pallor
Respiratory, thoracic and mediastinal disorders |  | Dyspnoea |  | Respiratory arrest Acute respiratory distress syndrome (ARDS) Pulmonary oedema Laryngeal oedema Pharyngeal oedema Bronchospasm Asthma Cough Hyperventilation Pharynx discomfort Laryngeal discomfort Rhinitis Dysphonia
Gastrointestinal disorders |  | Nausea Vomiting |  | Diarrhoea Abdominal pain Salivary hypersecretion Dysphagia Salivary gland enlargement
Skin and subcutaneous tissue disorders |  | Erythema Urticaria Pruritus | Rash | Acute generalized exanthematous pustulosis Angioedema Cold sweat Sweating increased
Musculoskeletal and connective tissue disorder |  |  | Back pain | Arthralgia
Renal and urinary disorders |  |  |  | Renal failure
General disorders and administration site conditions | Feeling hot | Chest pain Injection site warmth and pain | Asthenia Rigors Pyrexia | Injection site reaction** Coldness local Fatigue Malaise Thirst
Investigations |  |  | Blood creatinine increased | Electrocardiogram ST segment elevation Electrocardiogram abnormal
* Since the reactions were not observed during clinical trials with 4515 patients, best estimate is that their relative occurrence is rare (≥1/10,000 to <1/1000).
The most appropriate MedDRA term is used to describe a certain reaction and its symptoms and related conditions.
** Injection site reactions comprise injection site pain and swelling. In the majority of cases they are due to extravasation of contrast medium. These reactions are usually transient and result in recovery without sequelae. Cases of extravasation with inflammation, skin necrosis and even development of compartment syndrome have been reported.

As with other iodinated contrast media, very rare cases of mucocutaneous syndromes, including Stevens-Johnson syndrome, toxic epidermal necrolysis (Lyell syndrome) and erythema multiforme, have been reported following the administration of Iomeprol injection.

Paediatric patients

There is limited experience with paediatric patients. The clinical trial paediatric safety database comprises 167 patients.

The Iomeprol safety profile is similar in children and adults.

Reporting of suspected adverse reactions
Reporting suspected adverse reactions after authorisation of the medicinal product is important. It allows continued monitoring of the benefit/risk balance of the medicinal product. Healthcare professionals are asked to report any suspected adverse reactions via the Yellow Card Scheme
Website: www.mhra.gov.uk/yellowcard or search for MHRA Yellow Card in the Google Play or Apple App Store.

4.9 Overdose

The effects of overdose on the pulmonary and cardiovascular systems may become life-threatening. Treatment consists of support of the vital functions and prompt use of symptomatic therapy. Iomeprol does not bind to plasma or serum proteins and is therefore dialyzable.

5 PHARMACOLOGICAL PROPERTIES

5.1 Pharmacodynamic properties

ATC code: V08AB10

Iomeprol is a low osmolality, non-ionic organic molecule with radio-opacity conferred by an iodine content of 49% of the molecular weight. It is formulated for use as an intravascular/intracavitary/ intrathecal contrast medium in concentrations of up to 400mg iodine per ml. Even at this concentration the low viscosity allows delivery of high doses through thin catheters.

5.2 Pharmacokinetic properties

The pharmacokinetics of intravascularly administered Iomeprol are similar to those of other iodinated contrast media and conform to a two-compartment model with a rapid distribution and a slower elimination phase. In healthy subjects, the mean distribution and elimination half-lives of Iomeprol were 0.5 hours and 1.9 hours respectively.

Distribution volume is similar to that of extra cellular fluid. There is no significant serum protein binding and Iomeprol is not metabolized.

Elimination is almost exclusively through the kidneys (90% of the dose recovered in the urine within 96 hours of its administration) and is rapid (50% of an intravascularly administered dose within 2 hours).

5.3 Preclinical Safety Data

Pre-clinical data reveal no special hazard for humans based on conventional studies of safety pharmacology, repeated dose toxicity, genotoxicity, toxicity to reproduction.

Results from studies in rats, mice and dogs demonstrate that Iomeprol has an acute intravenous or intra-arterial toxicity similar to that of the other non ionic contrast media, as well as a good systemic tolerability after repeated intravenous administrations in rats and dogs.

6. PHARMACEUTICAL PARTICULARS

6.1 List of excipients

trometamol
hydrochloric acid
water for injection

6.2 Incompatibilities

In the absence of compatibility studies, this medicinal product must not be mixed with other medicinal products.

6.3 Shelf Life

Five years
The maximum use time after a bottle stopper has been pierced is 10 hours.

6.4 Special precautions for storage

Store below 30°C
Protect from light

6.5 Nature and contents of containers

Colourless type I or type II glass bottles with chlorobutyl or bromobutyl rubber stopper/aluminium cap containing 500 ml of solution.
Boxes of 1, 5 and 6 bottles.

6.6 Special precautions for disposal and other handling

Before use, examine the product to assure that the container and closure have not been damaged. Do not use the solution if it is discolored or particulate matter is present. The stopper should be pierced only once. The use of proper withdrawal cannulas for piercing the stopper and drawing up the contrast medium is recommended.
Multi-dose containers should be used only in conjunction with an automatic injector which has been approved for multipatient use.
After each patient, the connector between the injector and the patient should be replaced. All other devices should be replaced following the injector manufacturer’s instructions. In any case, strictly follow the manufacturer’s instructions.
Any unused product or waste material should be disposed of in accordance with local requirements.

7. MARKETING AUTHORISATION HOLDER

Bracco UK Ltd
Magdalen Centre
The Oxford Science Park
Oxford, OX4 4GA
United Kingdom

8. MARKETING AUTHORISATION NUMBER

PL 18920/0043

9. DATE OF FIRST AUTHORISATION/RENEWAL OF AUTHORISATION

14/11/2018

10. DATE OF REVISION OF THE TEXT

12/11/2021